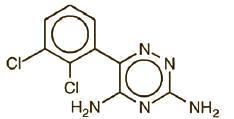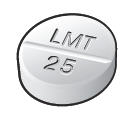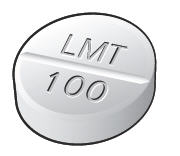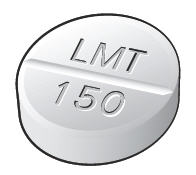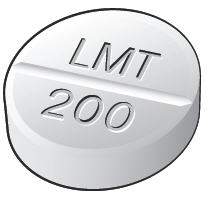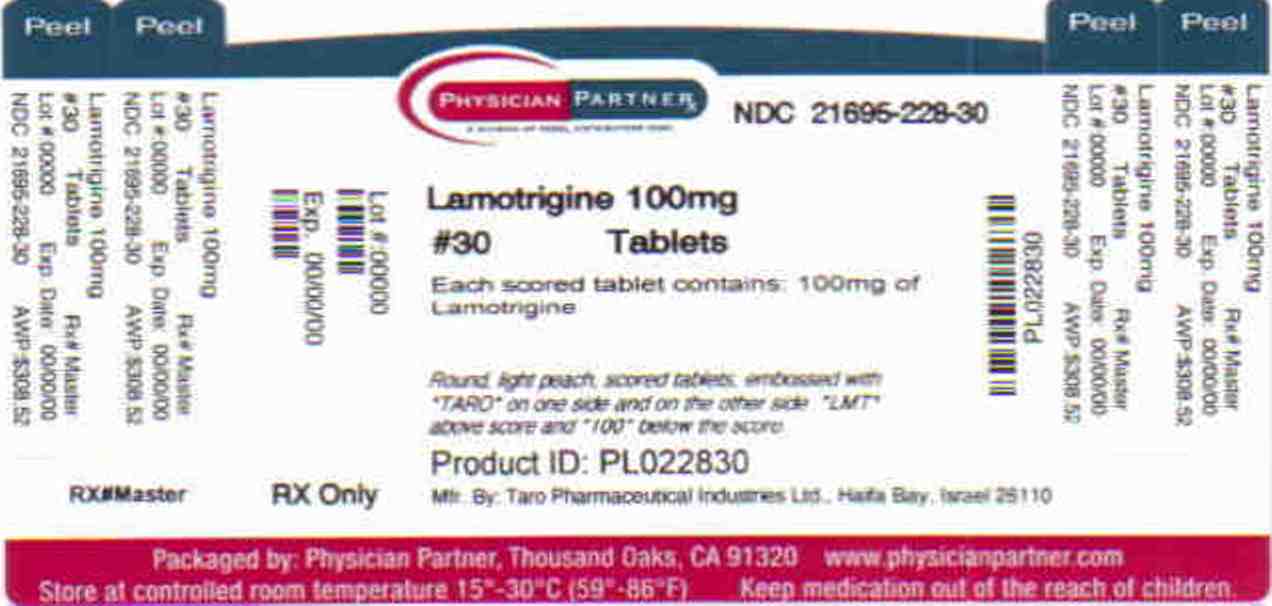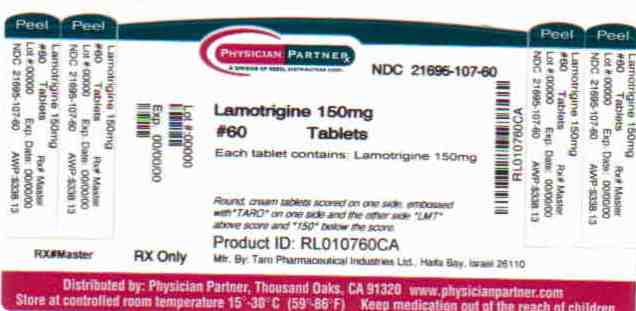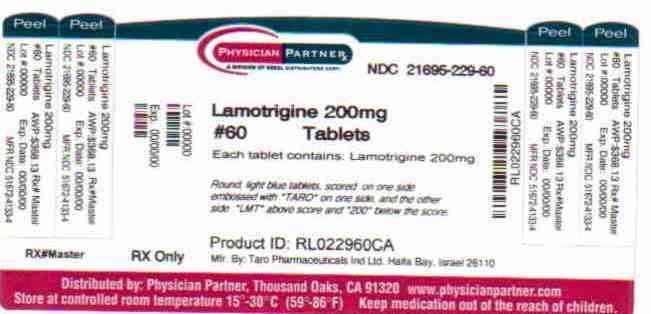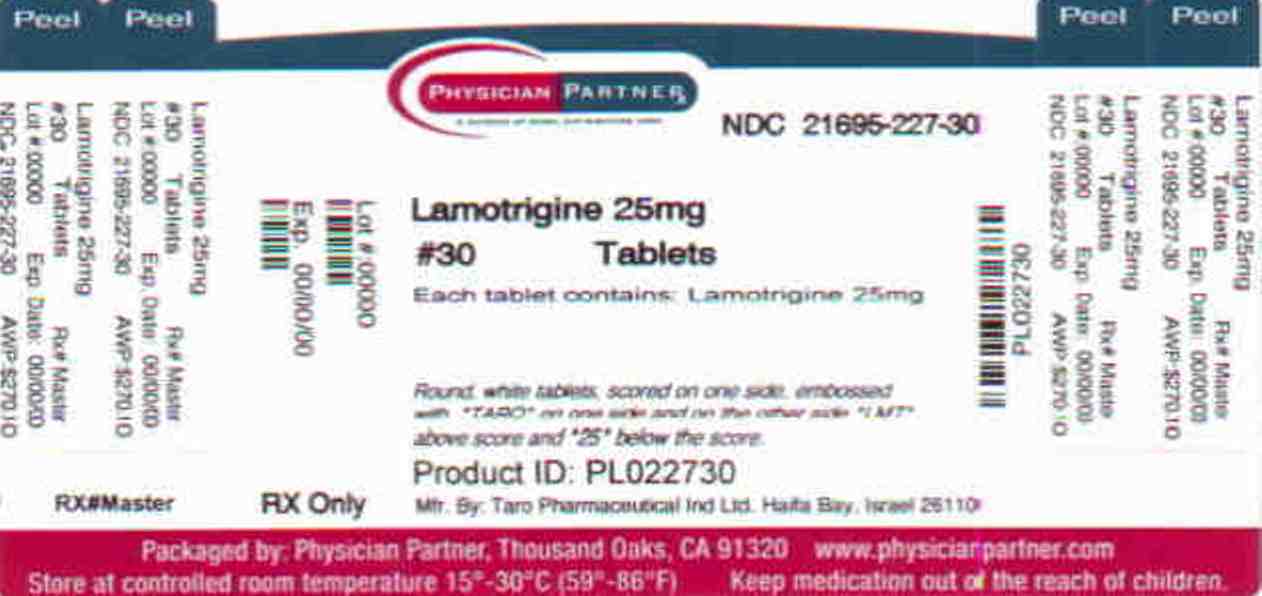 DRUG LABEL: Lamotrigine
NDC: 21695-227 | Form: TABLET
Manufacturer: Rebel Distributors Corp
Category: prescription | Type: HUMAN PRESCRIPTION DRUG LABEL
Date: 20100930

ACTIVE INGREDIENTS: Lamotrigine 25 mg/1 1
INACTIVE INGREDIENTS: Croscarmellose sodium; crospovidone; lactose monohydrate; magnesium stearate; cellulose, microcrystalline; povidone

HIGHLIGHTS OF PRESCRIBING INFORMATION

These highlights do not include all the information needed to use LAMOTRIGINE safely and effectively. See full prescribing information for LAMOTRIGINE.
LAMOTRIGINE Tablets
Initial U.S. Approval: 1994

RECENT MAJOR CHANGES

Warnings and Precautions, Suicidal Behavior and Ideation (5.5) | May/2009

BOXED WARNING

WARNING: SERIOUS SKIN RASHES

See full prescribing information for complete boxed warning.

Cases of life-threatening serious rashes, including Stevens-Johnson syndrome, toxic epidermal necrolysis, and/or rash-related death, have been caused by LAMOTRIGINE. The rate of serious rash is greater in pediatric patients than in adults. Additional factors that may increase the risk of rash include (5.1):

- coadministration with valproate
- exceeding recommended initial dose of LAMOTRIGINE
- exceeding recommended dose escalation of LAMOTRIGINE

Benign rashes are also caused by LAMOTRIGINE; however, it is not possible to predict which rashes will prove to be serious or life-threatening.

LAMOTRIGINE should be discontinued at the first sign of rash, unless the rash is clearly not drug-related. (5.1)

1 INDICATIONS AND USAGE

LAMOTRIGINE is an antiepileptic drug (AED) indicated for:

Epilepsy—adjunctive therapy in patients ≥2 years of age: (1.1)

- partial seizures.
- generalized seizures of Lennox-Gastaut syndrome.

Epilepsy—monotherapy in patients ≥16 years of age: conversion to monotherapy in patients with partial seizures who are receiving treatment with carbamazepine, phenobarbital, phenytoin, primidone, or valproate as the single AED. (1.1)

Bipolar Disorder in patients ≥18 years of age: maintenance treatment of Bipolar I Disorder to delay the time to occurrence of mood episodes in patients treated for acute mood episodes with standard therapy. (1.2)

2 DOSAGE AND ADMINISTRATION

- Dosing is based on concomitant medications, indication, and patient age. (2.2, 2.4)
- To avoid an increased risk of rash, the recommended initial dose and subsequent dose escalations should not be exceeded. LAMOTRIGINE Starter Kits are available for the first 5 weeks of treatment. (2.1, 16)
- Do not restart LAMOTRIGINE in patients who discontinued due to rash unless the potential benefits clearly outweigh the risks. (2.1)
- Adjustments to maintenance doses will in most cases be required in patients starting or stopping estrogen-containing oral contraceptives. (2.1, 5.8)
- LAMOTRIGINE should be discontinued over a period of at least 2 weeks (approximately 50% reduction per week). (2.1, 5.9)

Epilepsy

- Adjunctive therapy—See Table 1 for patients >12 years of age and Tables 2 and 3 for patients 2 to 12 years. (2.2)
- Conversion to monotherapy—See Table 4. (2.3)

Bipolar Disorder: See Tables 5 and 6. (2.4)

3 DOSAGE FORMS AND STRENGTHS

- Tablets: 25 mg, 100 mg, 150 mg, and 200 mg scored. (3.1, 16)

4 CONTRAINDICATIONS

Hypersensitivity to the drug or its ingredients. (Boxed Warning, 4)

5 WARNINGS AND PRECAUTIONS

- Life-threatening serious rash and/or rash-related death may result. (Boxed Warning, 5.1)
- Hypersensitivity reaction may be fatal or life-threatening. Early signs of hypersensitivity (e.g., fever, lymphadenopathy) may present without rash; if signs present, patient should be evaluated immediately.LAMOTRIGINE should be discontinued if alternate etiology for hypersensitivity signs is not found. (5.2)
- Acute multiorgan failure has resulted (some cases fatal). (5.3)
- Blood dyscrasias (e.g., neutropenia, thrombocytopenia, pancytopenia), may result either with or without an associated hypersensitivity syndrome. (5.4)
- Suicidal behavior and ideation. (5.5)
- Clinical worsening, emergence of new symptoms, and suicidal ideation/behaviors may be associated with treatment of bipolar disorder. Patients should be closely monitored, particularly early in treatment or during dosage changes. (5.6)
- Medication errors involving LAMOTRIGINE have occurred. In particular the name lamotrigine can be confused with names of other commonly used medications. Medication errors may also occur between the different formulations of LAMOTRIGINE. (3.4, 5.7, 16, 17.9)

6 ADVERSE REACTIONS

- Most common adverse reactions (incidence ≥10%) in adult epilepsy clinical studies were dizziness, headache, diplopia, ataxia, nausea, blurred vision, somnolence, rhinitis, and rash. Additional adverse reactions (incidence ≥10%) reported in children in epilepsy clinical studies included vomiting, infection, fever, accidental injury, pharyngitis, abdominal pain, and tremor. (6.1)
- Most common adverse reactions (incidence >5%) in adult bipolar clinical studies were nausea, insomnia, somnolence, back pain, fatigue, rash, rhinitis, abdominal pain, and xerostomia. (6.1)

To report SUSPECTED ADVERSE REACTIONS, contact the FDA at 1-800-FDA-1088 or www.fda.gov/medwatch.

7 DRUG INTERACTIONS

- Valproate increases lamotrigine concentrations more than 2-fold. (7, 12.3)
- Carbamazepine, phenytoin, phenobarbital, and primidone decrease lamotrigine concentrations by approximately 40%. (7, 12.3)
- Oral estrogen-containing contraceptives and rifampin also decrease lamotrigine concentrations by approximately 50%. (7, 12.3)

8 USE IN SPECIFIC POPULATIONS

- Hepatic impairment: Dosage adjustments required. (2.1)
- Healthcare professionals can enroll patients in the Lamotrigine Pregnancy Registry (1-800-336-2176). Patients can enroll themselves in the North American Antiepileptic Drug Pregnancy Registry (1-888-233-2334). (8.1)
- Efficacy of LAMOTRIGINE, used as adjunctive treatment for partial seizures, was not demonstrated in a small randomized, double-blind, placebo-controlled study in very young pediatric patients (1 to 24 months). (8.4)

FULL PRESCRIBING INFORMATION

BOXED WARNING

LAMOTRIGINE can cause serious rashes requiring hospitalization and discontinuation of treatment. The incidence of these rashes, which have included Stevens-Johnson syndrome, is approximately 0.8% (8 per 1,000) in pediatric patients (2 to 16 years of age) receiving LAMOTRIGINE as adjunctive therapy for epilepsy and 0.3% (3 per 1,000) in adults on adjunctive therapy for epilepsy. In clinical trials of bipolar and other mood disorders, the rate of serious rash was 0.08% (0.8 per 1,000) in adult patients receiving LAMOTRIGINE as initial monotherapy and 0.13% (1.3 per 1,000) in adult patients receiving LAMOTRIGINE as adjunctive therapy. In a prospectively followed cohort of 1,983 pediatric patients (2 to 16 years of age) with epilepsy taking adjunctive LAMOTRIGINE, there was 1 rash-related death. In worldwide postmarketing experience, rare cases of toxic epidermal necrolysis and/or rash-related death have been reported in adult and pediatric patients, but their numbers are too few to permit a precise estimate of the rate.

Other than age, there are as yet no factors identified that are known to predict the risk of occurrence or the severity of rash caused by LAMOTRIGINE. There are suggestions, yet to be proven, that the risk of rash may also be increased by (1) coadministration of LAMOTRIGINE with valproate (includes valproic acid and divalproex sodium), (2) exceeding the recommended initial dose of LAMOTRIGINE, or (3) exceeding the recommended dose escalation for LAMOTRIGINE. However, cases have occurred in the absence of these factors. Nearly all cases of life-threatening rashes caused by LAMOTRIGINE have occurred within 2 to 8 weeks of treatment initiation. However, isolated cases have occurred after prolonged treatment (e.g., 6 months). Accordingly, duration of therapy cannot be relied upon as means to predict the potential risk heralded by the first appearance of a rash.

Although benign rashes are also caused by LAMOTRIGINE, it is not possible to predict reliably which rashes will prove to be serious or life-threatening. Accordingly, LAMOTRIGINE should ordinarily be discontinued at the first sign of rash, unless the rash is clearly not drug-related. Discontinuation of treatment may not prevent a rash from becoming life-threatening or permanently disabling or disfiguring [see Warnings and Precautions (5.1)].

1 INDICATIONS AND USAGE

1.1 Epilepsy

Adjunctive Therapy: LAMOTRIGINE is indicated as adjunctive therapy for the following seizure types in patients ≥2 years of age:

- partial seizures
- generalized seizures of Lennox-Gastaut syndrome

Monotherapy: LAMOTRIGINE is indicated for conversion to monotherapy in adults (≥16 years of age) with partial seizures who are receiving treatment with carbamazepine, phenytoin, phenobarbital, primidone, or valproate as the single antiepileptic drug (AED).

Safety and effectiveness of LAMOTRIGINE have not been established (1) as initial monotherapy; (2) for conversion to monotherapy from AEDs other than carbamazepine, phenytoin, phenobarbital, primidone, or valproate; or (3) for simultaneous conversion to monotherapy from 2 or more concomitant AEDs.

1.2 Bipolar Disorder

LAMOTRIGINE is indicated for the maintenance treatment of Bipolar I Disorder to delay the time to occurrence of mood episodes (depression, mania, hypomania, mixed episodes) in adults (≥18 years of age) treated for acute mood episodes with standard therapy. The effectiveness of LAMOTRIGINE in the acute treatment of mood episodes has not been established.

The effectiveness of LAMOTRIGINE as maintenance treatment was established in 2 placebo-controlled trials in patients with Bipolar I Disorder as defined by DSM-IV [see Clinical Studies (14.2)]. The physician who elects to prescribe LAMOTRIGINE for periods extending beyond 16 weeks should periodically re-evaluate the long-term usefulness of the drug for the individual patient.

2 DOSAGE AND ADMINISTRATION

2.1 General Dosing Considerations

Rash: There are suggestions, yet to be proven, that the risk of severe, potentially life-threatening rash may be increased by (1) coadministration of LAMOTRIGINE with valproate, (2) exceeding the recommended initial dose of LAMOTRIGINE, or (3) exceeding the recommended dose escalation for LAMOTRIGINE. However, cases have occurred in the absence of these factors [see Boxed Warning]. Therefore, it is important that the dosing recommendations be followed closely.

The risk of nonserious rash may be increased when the recommended initial dose and/or the rate of dose escalation of LAMOTRIGINE is exceeded and in patients with a history of allergy or rash to other AEDs.

LAMOTRIGINE Starter Kits provide LAMOTRIGINE at doses consistent with the recommended titration schedule for the first 5 weeks of treatment, based upon concomitant medications for patients with epilepsy (>12 years of age) and Bipolar I Disorder (≥18 years of age) and are intended to help reduce the potential for rash. The use of LAMOTRIGINE Starter Kits is recommended for appropriate patients who are starting or restarting LAMOTRIGINE [see How Supplied/Storage and Handling (16)].

It is recommended that LAMOTRIGINE not be restarted in patients who discontinued due to rash associated with prior treatment with lamotrigine, unless the potential benefits clearly outweigh the risks. If the decision is made to restart a patient who has discontinued lamotrigine, the need to restart with the initial dosing recommendations should be assessed. The greater the interval of time since the previous dose, the greater consideration should be given to restarting with the initial dosing recommendations. If a patient has discontinued lamotrigine for a period of more than 5 half-lives, it is recommended that initial dosing recommendations and guidelines be followed. The half-life of lamotrigine is affected by other concomitant medications [see Clinical Pharmacology (12.3)].

LAMOTRIGINE Added to Drugs Known to Induce or Inhibit Glucuronidation: Drugs other than those listed in the Clinical Pharmacology section [see Clinical Pharmacology (12.3)] have not been systematically evaluated in combination with lamotrigine. Because lamotrigine is metabolized predominantly by glucuronic acid conjugation, drugs that are known to induce or inhibit glucuronidation may affect the apparent clearance of lamotrigine and doses of LAMOTRIGINE may require adjustment based on clinical response.

Target Plasma Levels for Patients With Epilepsy or Bipolar Disorder: A therapeutic plasma concentration range has not been established for lamotrigine. Dosing of LAMOTRIGINE should be based on therapeutic response [see Clinical Pharmacology (12.3)].

Women Taking Estrogen-Containing Oral Contraceptives: Starting LAMOTRIGINE in Women Taking Estrogen-Containing Oral Contraceptives: Although estrogen-containing oral contraceptives have been shown to increase the clearance of lamotrigine [see Clinical Pharmacology (12.3)], no adjustments to the recommended dose-escalation guidelines for LAMOTRIGINE should be necessary solely based on the use of estrogen-containing oral contraceptives. Therefore, dose escalation should follow the recommended guidelines for initiating adjunctive therapy with LAMOTRIGINE based on the concomitant AED or other concomitant medications (see Table 1 or Table 5). See below for adjustments to maintenance doses of LAMOTRIGINE in women taking estrogen-containing oral contraceptives.

Adjustments to the Maintenance Dose of LAMOTRIGINE In Women Taking Estrogen-Containing Oral Contraceptives:

(1) Taking Estrogen-Containing Oral Contraceptives: For women not taking carbamazepine, phenytoin, phenobarbital, primidone, or rifampin, the maintenance dose of LAMOTRIGINE will in most cases need to be increased, by as much as 2-fold over the recommended target maintenance dose, in order to maintain a consistent lamotrigine plasma level [see Clinical Pharmacology (12.3)].

(2) Starting Estrogen-Containing Oral Contraceptives: In women taking a stable dose of LAMOTRIGINE and not taking carbamazepine, phenytoin, phenobarbital, primidone, or rifampin, the maintenance dose will in most cases need to be increased by as much as 2-fold in order to maintain a consistent lamotrigine plasma level. The dose increases should begin at the same time that the oral contraceptive is introduced and continue, based on clinical response, no more rapidly than 50 to 100 mg/day every week. Dose increases should not exceed the recommended rate (see Table 1 or Table 5) unless lamotrigine plasma levels or clinical response support larger increases. Gradual transient increases in lamotrigine plasma levels may occur during the week of inactive hormonal preparation ("pill-free" week), and these increases will be greater if dose increases are made in the days before or during the week of inactive hormonal preparation. Increased lamotrigine plasma levels could result in additional adverse reactions, such as dizziness, ataxia, and diplopia. If adverse reactions attributable to LAMOTRIGINE consistently occur during the "pill-free" week, dose adjustments to the overall maintenance dose may be necessary. Dose adjustments limited to the "pill-free" week are not recommended. For women taking LAMOTRIGINE in addition to carbamazepine, phenytoin, phenobarbital, primidone, or rifampin, no adjustment should be necessary to the dose of LAMOTRIGINE.

(3) Stopping Estrogen-Containing Oral Contraceptives: For women not taking carbamazepine, phenytoin, phenobarbital, primidone, or rifampin, the maintenance dose of LAMOTRIGINE will in most cases need to be decreased by as much as 50% in order to maintain a consistent lamotrigine plasma level. The decrease in dose of LAMOTRIGINE should not exceed 25% of the total daily dose per week over a 2-week period, unless clinical response or lamotrigine plasma levels indicate otherwise [see Clinical Pharmacology (12.3)]. For women taking LAMOTRIGINE in addition to carbamazepine, phenytoin, phenobarbital, primidone, or rifampin, no adjustment to the dose of LAMOTRIGINE should be necessary.

Women and Other Hormonal Contraceptive Preparations or Hormone Replacement Therapy: The effect of other hormonal contraceptive preparations or hormone replacement therapy on the pharmacokinetics of lamotrigine has not been systematically evaluated. It has been reported that ethinylestradiol, not progestogens, increased the clearance of lamotrigine up to 2-fold, and the progestin-only pills had no effect on lamotrigine plasma levels. Therefore, adjustments to the dosage of LAMOTRIGINE in the presence of progestogens alone will likely not be needed.

Patients With Hepatic Impairment: Experience in patients with hepatic impairment is limited. Based on a clinical pharmacology study in 24 patients with mild, moderate, and severe liver impairment [see Use in Specific Populations (8.6), Clinical Pharmacology (12.3)], the following general recommendations can be made. No dosage adjustment is needed in patients with mild liver impairment. Initial, escalation, and maintenance doses should generally be reduced by approximately 25% in patients with moderate and severe liver impairment without ascites and 50% in patients with severe liver impairment with ascites. Escalation and maintenance doses may be adjusted according to clinical response.

Patients With Renal Impairment: Initial doses of LAMOTRIGINE should be based on patients' concomitant medications (see Tables 1-3 or Table 5); reduced maintenance doses may be effective for patients with significant renal impairment [see Use in Specific Populations (8.7), Clinical Pharmacology (12.3)]. Few patients with severe renal impairment have been evaluated during chronic treatment with LAMOTRIGINE. Because there is inadequate experience in this population, LAMOTRIGINE should be used with caution in these patients.

Discontinuation Strategy: Epilepsy: For patients receiving LAMOTRIGINE in combination with other AEDs, a re-evaluation of all AEDs in the regimen should be considered if a change in seizure control or an appearance or worsening of adverse reactions is observed.

If a decision is made to discontinue therapy with LAMOTRIGINE, a step-wise reduction of dose over at least 2 weeks (approximately 50% per week) is recommended unless safety concerns require a more rapid withdrawal [see Warnings and Precautions (5.9)].

Discontinuing carbamazepine, phenytoin, phenobarbital, or primidone should prolong the half-life of lamotrigine; discontinuing valproate should shorten the half-life of lamotrigine.

Bipolar Disorder: In the controlled clinical trials, there was no increase in the incidence, type, or severity of adverse reactions following abrupt termination of LAMOTRIGINE. In clinical trials in patients with Bipolar Disorder, 2 patients experienced seizures shortly after abrupt withdrawal of LAMOTRIGINE. However, there were confounding factors that may have contributed to the occurrence of seizures in these bipolar patients. Discontinuation of LAMOTRIGINE should involve a step-wise reduction of dose over at least 2 weeks (approximately 50% per week) unless safety concerns require a more rapid withdrawal [see Warnings and Precautions (5.9)].

2.2 Epilepsy – Adjunctive Therapy

This section provides specific dosing recommendations for patients greater than 12 years of age and patients 2 to 12 years of age. Within each of these age-groups, specific dosing recommendations are provided depending upon concomitant AED or other concomitant medications (Table 1 for patients greater than 12 years of age and Table 2 for patients 2 to 12 years of age). A weight-based dosing guide for patients 2 to 12 years of age on concomitant valproate is provided in Table 3.

Patients Over 12 Years of Age: Recommended dosing guidelines are summarized in Table 1.

Table 1. Escalation Regimen for LAMOTRIGINE in Patients Over 12 Years of Age With Epilepsy
 | For Patients Taking Valproate [Valproate has been shown to inhibit glucuronidation and decrease the apparent clearance of lamotrigine [see Drug Interactions (7), Pharmacokinetics (12.3)].] | For Patients Taking AEDs Other Than Carbamazepine, Phenytoin, Phenobarbital, or Primidone [These drugs induce glucuronidation and increase clearance [see Drug Interactions (7), Pharmacokinetics (12.3)]. Other drugs which have similar effects include estrogen-containing oral contraceptives and rifampin [see Drug Interactions (7), Pharmacokinetics (12.3)].] , and Not Taking Valproate | For Patients Taking Carbamazepine, Phenytoin, Phenobarbital, or Primidone and Not Taking Valproate
Weeks 1 and 2 | 25 mg every other day | 25 mg every day | 50 mg/day
Weeks 3 and 4 | 25 mg every day | 50 mg/day | 100 mg/day (in 2 divided doses)
Weeks 5 onwards to maintenance | Increase by 25 to 50 mg/day every 1 to 2 weeks | Increase by 50 mg/day every 1 to 2 weeks | Increase by 100 mg/day every 1 to 2 weeks.
Usual Maintenance Dose | 100 to 200 mg/day with valproate alone 100 to 400 mg/day with valproate and other drugs that induce glucuronication (in 1 or 2 divided doses) | 225 to 375 mg/day (in 2 divided doses) | 300 to 500 mg/day (in 2 divided doses)

Dosing recommendations for oral contraceptives can be found in General Dosing Considerations [see Dosage and Administration (2.1)]. Patients on rifampin should follow the same dosing titration/maintenance regimen used with drugs that induce glucuronidation and increase clearance.

Patients 2 to 12 Years of Age: Recommended dosing guidelines are summarized in Table 2.

Smaller starting doses and slower dose escalations than those used in clinical trials are recommended because of the suggestion that the risk of rash may be decreased by smaller starting doses and slower dose escalations. Therefore, maintenance doses will take longer to reach in clinical practice than in clinical trials. It may take several weeks to months to achieve an individualized maintenance dose. Maintenance doses in patients weighing less than 30 kg, regardless of age or concomitant AED, may need to be increased as much as 50%, based on clinical response.

Table 2. Escalation Regimen for LAMOTRIGINE in Patients 2 to 12 Years of Age With Epilepsy
 | For Patients Taking Valproate [Valproate has been shown to inhibit glucuronidation and decrease the apparent clearance of lamotrigine [see Drug Interactions (7), Pharmacokinetics (12.3)].] | For Patients Taking AEDs Other Than Carbamazepine, Phenytoin, Phenobarbital, or Primidone [These drugs induce glucuronidation and increase clearance [see Drug Interactions (7), Pharmacokinetics (12.3)]. Other drugs which have similar effects include estrogen-containing oral contraceptives and rifampin [see Drug Interactions (7), Pharmacokinetics (12.3)].] , and Not Taking Valproate | For Patients Taking Carbamazepine, Phenytoin, Phenobarbital, or Primidone and Not Taking Valproate
Weeks 1 and 2 | 0.15 mg/kg/day in 1 or 2 divided doses, rounded down to the nearest whole tablet (see Table 3 for weight based dosing guide) | 0.3 mg/kg/day in 1 or 2 divided doses, rounded down to the nearest whole tablet | 0.6 mg/kg/day in 2 divided doses, rounded down to the nearest whole tablet
Weeks 3 and 4 | 0.3 mg/kg/day in 1 or 2 divided doses, rounded down to the nearest whole tablet (see Table 3 for weight based dosing guide) | 0.6 mg/kg/day in 2 divided doses, rounded down to the nearest whole tablet | 1.2 mg/kg/day in 2 divided doses, rounded down to the nearest whole tablet
Weeks 5 onwards to maintenance | The dose should be increased every 1 to 2 weeks as follows: calculate 0.3 mg/kg/day, round this amount down to the nearest whole tablet, and add this amount to the previously administered daily dose | The dose should be increased every 1 to 2 weeks as follows: calculate 0.6 mg/kg/day, round this amount down to the nearest whole tablet, and add this amount to the previously administered daily dose | The dose should be increased every 1 to 2 weeks as follows: calculate 1.2 mg/kg/day, round this amount down to the nearest whole tablet, and add this amount to the previously administered daily dose
Usual Maintenance Dose | 1 to 5 mg/kg/day (maximum 200 mg/day in 1 or 2 divided doses). 1 to 3 mg/kg/day with valproate alone | 4.5 to 7.5 mg/kg/day (maximum 300 mg/day in 2 divided doses) | 5 to 15 mg/kg/day (maximum 400 mg/day in 2 divided doses)
Maintenance dose in patients less than 30 kg | May need to be increased by as much as 50%, based on clinical response | May need to be increased by as much as 50%, based on clinical response | May need to be increased by as much as 50%, based on clinical response
Note: Only whole tablets should be used for dosing.

Dosing recommendations for oral contraceptives can be found in General Dosing Considerations [see Dosage and Administration (2.1)]. Patients on rifampin should follow the same dosing titration/maintenance regimen used with drugs that induce glucuronidation and increase clearance.

Table 3. The Initial Weight-Based Dosing Guide for Patients 2 to 12 Years Taking Valproate (Weeks 1 to 4) With Epilepsy
If the patient's weight is |  | Give this daily dose, using the most appropriate combination of LAMOTRIGINE 2-mg and 5-mg tablets
Greater than | And less than | Weeks 1 and 2 | Weeks 3 and 4
6.7 kg | 14 kg | 2 mg every other day | 2 mg every day
14.1 kg | 27 kg | 2 mg every day | 4 mg every day
27.1 kg | 34 kg | 4 mg every day | 8 mg every day
34.1 kg | 40 kg | 5 mg every day | 10 mg every day

Usual Adjunctive Maintenance Dose for Epilepsy: The usual maintenance doses identified in Tables 1 and 2 are derived from dosing regimens employed in the placebo-controlled adjunctive studies in which the efficacy of LAMOTRIGINE was established. In patients receiving multidrug regimens employing carbamazepine, phenytoin, phenobarbital, or primidone without valproate, maintenance doses of adjunctive LAMOTRIGINE as high as 700 mg/day have been used. In patients receiving valproate alone, maintenance doses of adjunctive LAMOTRIGINE as high as 200 mg/day have been used. The advantage of using doses above those recommended in Tables 1 through 4 has not been established in controlled trials.

2.3 Epilepsy – Conversion From Adjunctive Therapy to Monotherapy

The goal of the transition regimen is to effect the conversion to monotherapy with LAMOTRIGINE under conditions that ensure adequate seizure control while mitigating the risk of serious rash associated with the rapid titration of LAMOTRIGINE.

The recommended maintenance dose of LAMOTRIGINE as monotherapy is 500 mg/day given in 2 divided doses.

To avoid an increased risk of rash, the recommended initial dose and subsequent dose escalations of LAMOTRIGINE should not be exceeded [see Boxed Warning].

Conversion From Adjunctive Therapy With Carbamazepine, Phenytoin, Phenobarbital, or Primidone to Monotherapy With LAMOTRIGINE: After achieving a dose of 500 mg/day of LAMOTRIGINE according to the guidelines in Table 1, the concomitant AED should be withdrawn by 20% decrements each week over a 4-week period. The regimen for the withdrawal of the concomitant AED is based on experience gained in the controlled monotherapy clinical trial.

Conversion from Adjunctive Therapy With Valproate to Monotherapy With LAMOTRIGINE: The conversion regimen involves 4 steps outlined in Table 4.

Table 4. Conversion From Adjunctive Therapy With Valproate to Monotherapy With LAMOTRIGINE in Patients ≥16 Years of Age with Epilepsy
 | LAMOTRIGINE | Valproate
Step 1 | Achieve a dose of 200 mg/day according to guidelines in Table 1 (if not already on200 mg/day). | Maintain previous stable dose.
Step 2 | Maintain at 200 mg/day. | Decrease to 500 mg/day by decrements no greater than 500 mg/day/week and then maintain the dose of 500 mg/day for 1 week.
Step 3 | Increase to 300 mg/day and maintain for 1 week. | Simultaneously decrease to 250 mg/day and maintain for 1 week.
Step 4 | Increase by 100 mg/day every week to achieve maintenance dose of 500 mg/day. | Discontinue.

Conversion from Adjunctive Therapy With AEDs Other Than Carbamazepine, Phenytoin, Phenobarbital, Primidone, or Valproate to Monotherapy With LAMOTRIGINE: No specific dosing guidelines can be provided for conversion to monotherapy with LAMOTRIGINE with AEDs other than carbamazepine, phenobarbital, phenytoin, primidone, or valproate.

2.4 Bipolar Disorder

The goal of maintenance treatment with LAMOTRIGINE is to delay the time to occurrence of mood episodes (depression, mania, hypomania, mixed episodes) in patients treated for acute mood episodes with standard therapy. The target dose of LAMOTRIGINE is 200 mg/day (100 mg/day in patients taking valproate, which decreases the apparent clearance of lamotrigine, and 400 mg/day in patients not taking valproate and taking either carbamazepine, phenytoin, phenobarbital, primidone, or rifampin, which increase the apparent clearance of lamotrigine). In the clinical trials, doses up to 400 mg/day as monotherapy were evaluated; however, no additional benefit was seen at 400 mg/day compared with 200 mg/day [see Clinical Studies (14.2)]. Accordingly, doses above 200 mg/day are not recommended. Treatment with LAMOTRIGINE is introduced, based on concurrent medications, according to the regimen outlined in Table 5. If other psychotropic medications are withdrawn following stabilization, the dose of LAMOTRIGINE should be adjusted. For patients discontinuing valproate, the dose of LAMOTRIGINE should be doubled over a 2-week period in equal weekly increments (see Table 6). For patients discontinuing carbamazepine, phenytoin, phenobarbital, primidone, or rifampin, the dose of LAMOTRIGINE should remain constant for the first week and then should be decreased by half over a 2-week period in equal weekly decrements (see Table 6). The dose of LAMOTRIGINE may then be further adjusted to the target dose (200 mg) as clinically indicated.

If other drugs are subsequently introduced, the dose of LAMOTRIGINE may need to be adjusted. In particular, the introduction of valproate requires reduction in the dose of LAMOTRIGINE [see Drug Interactions (7), Clinical Pharmacology (12.3)].

To avoid an increased risk of rash, the recommended initial dose and subsequent dose escalations of LAMOTRIGINE should not be exceeded [see Boxed Warning].

Table 5. Escalation Regimen for LAMOTRIGINE for Patients With Bipolar Disorder [See Drug Interactions (7) and Clinical Pharmacology (12.3) for a description of known drug interactions.]
 | For Patients Taking Valproate [Valproate has been shown to decrease the apparent clearance of lamotrigine.] | For Patients Not Taking Carbamazepine, Phenytoin, Phenobarbital, Primidone, or Rifampin [Carbamazepine, phenytoin, phenobarbital, primidone, and rifampin have been shown to increase the apparent clearance of lamotrigine.] and Not Taking Valproate | For Patients Taking Carbamazepine, Phenytoin, Phenobarbital, Primidone, or Rifampin and Not Taking Valproate
Weeks 1 and 2 | 25 mg every other day | 25 mg daily | 50 mg daily
Weeks 3 and 4 | 25 mg daily | 50 mg daily | 100 mg daily, in divided doses
Week 5 | 50 mg daily | 100 mg daily | 200 mg daily, in divided doses
Week 6 | 100 mg daily | 200 mg daily | 300 mg daily, in divided doses
Week 7 | 100 mg daily | 200 mg daily | up to 400 mg daily, in divided doses

Table 6. Dosage Adjustments to LAMOTRIGINE for Patients With Bipolar Disorder Following Discontinuation of Psychotropic Medications [See Drug Interactions (7) and Clinical Pharmacology (12.3) for a description of known drug interactions.]
 | Discontinuation of Psychotropic Drugs (excluding Carbamazepine, Phenytoin, Phenobarbital, Primidone, Rifampin [Carbamazepine, phenytoin, phenobarbital, primidone, and rifampin have been shown to increase the apparent clearance of lamotrigine.] , or Valproate [Valproate has been shown to decrease the apparent clearance of lamotrigine.]) | After Discontinuation of Valproate | After Discontinuation of Carbamazepine, Phenytoin, Phenobarbital, Primidone, or Rifampin
 | Discontinuation of Psychotropic Drugs (excluding Carbamazepine, Phenytoin, Phenobarbital, Primidone, Rifampin [Carbamazepine, phenytoin, phenobarbital, primidone, and rifampin have been shown to increase the apparent clearance of lamotrigine.] , or Valproate [Valproate has been shown to decrease the apparent clearance of lamotrigine.]) | Current dose of LAMOTRIGINE (mg/day) 100 | Current dose of LAMOTRIGINE (mg/day) 400
Week 1 | Maintain current dose of LAMOTRIGINE | 150 | 400
Week 2 | Maintain current dose of LAMOTRIGINE | 200 | 300
Week 3 onward | Maintain current dose of LAMOTRIGINE | 200 | 200

The benefit of continuing treatment in patients who had been stabilized in an 8- to 16-week open-label phase with LAMOTRIGINE was established in 2 randomized, placebo-controlled clinical maintenance trials [see Clinical Studies (14.2)]. However, the optimal duration of treatment with LAMOTRIGINE has not been established. Thus, patients should be periodically reassessed to determine the need for maintenance treatment.

3 DOSAGE FORMS AND STRENGTHS

3.1 Tablets

25 mg, round, white tablets, scored on one side, embossed with "TARO" on one side and on the other side "LMT" above score and "25" below the score.

100 mg, round, light peach, scored tablets, embossed with "TARO" on one side and on the other side "LMT" above score and "100" below the score.

150 mg, round, cream tablets, scored on one side, embossed with "TARO" on one side and on the other side "LMT" above score and "150" below the score.

200 mg, round, light blue tablets, scored on one side, embossed with "TARO" on one side and on the other side "LMT" above score and "200" below the score.

3.4 Potential Medication Errors

Patients should be strongly advised to visually inspect their tablets to verify that they are receiving LAMOTRIGINE as well as the correct formulation of LAMOTRIGINE each time they fill their prescription. Depictions of the LAMOTRIGINE Tablets can be found in the Medication Guide that accompanies the product.

4 CONTRAINDICATIONS

LAMOTRIGINE is contraindicated in patients who have demonstrated hypersensitivity to the drug or its ingredients [see Boxed Warning].

5 WARNINGS AND PRECAUTIONS

5.1 Serious Skin Rashes

[see Boxed Warning]

Pediatric Population: The incidence of serious rash associated with hospitalization and discontinuation of LAMOTRIGINE in a prospectively followed cohort of pediatric patients (2 to 16 years of age) with epilepsy receiving adjunctive therapy was approximately 0.8% (16 of 1,983). When 14 of these cases were reviewed by 3 expert dermatologists, there was considerable disagreement as to their proper classification. To illustrate, one dermatologist considered none of the cases to be Stevens-Johnson syndrome; another assigned 7 of the 14 to this diagnosis. There was 1 rash-related death in this 1,983-patient cohort. Additionally, there have been rare cases of toxic epidermal necrolysis with and without permanent sequelae and/or death in US and foreign postmarketing experience.

There is evidence that the inclusion of valproate in a multidrug regimen increases the risk of serious, potentially life-threatening rash in pediatric patients. In pediatric patients who used valproate concomitantly, 1.2% (6 of 482) experienced a serious rash compared with 0.6% (6 of 952) patients not taking valproate.

Adult Population: Serious rash associated with hospitalization and discontinuation of LAMOTRIGINE occurred in 0.3% (11 of 3,348) of adult patients who received LAMOTRIGINE in premarketing clinical trials of epilepsy. In the bipolar and other mood disorders clinical trials, the rate of serious rash was 0.08% (1 of 1,233) of adult patients who received LAMOTRIGINE as initial monotherapy and 0.13% (2 of 1,538) of adult patients who received LAMOTRIGINE as adjunctive therapy. No fatalities occurred among these individuals. However, in worldwide postmarketing experience, rare cases of rash-related death have been reported, but their numbers are too few to permit a precise estimate of the rate.

Among the rashes leading to hospitalization were Stevens-Johnson syndrome, toxic epidermal necrolysis, angioedema, and a rash associated with a variable number of the following systemic manifestations: fever, lymphadenopathy, facial swelling, and hematologic and hepatologic abnormalities.

There is evidence that the inclusion of valproate in a multidrug regimen increases the risk of serious, potentially life-threatening rash in adults. Specifically, of 584 patients administered LAMOTRIGINE with valproate in epilepsy clinical trials, 6 (1%) were hospitalized in association with rash; in contrast, 4 (0.16%) of 2,398 clinical trial patients and volunteers administered LAMOTRIGINE in the absence of valproate were hospitalized.

Patients With History of Allergy or Rash to Other AEDs: The risk of nonserious rash may be increased when the recommended initial dose and/or the rate of dose escalation of LAMOTRIGINE is exceeded and in patients with a history of allergy or rash to other AEDs.

5.2 Hypersensitivity Reactions

Hypersensitivity reactions, some fatal or life-threatening, have also occurred. Some of these reactions have included clinical features of multiorgan failure/dysfunction, including hepatic abnormalities and evidence of disseminated intravascular coagulation. It is important to note that early manifestations of hypersensitivity (e.g., fever, lymphadenopathy) may be present even though a rash is not evident. If such signs or symptoms are present, the patient should be evaluated immediately. LAMOTRIGINE should be discontinued if an alternative etiology for the signs or symptoms cannot be established.

Prior to initiation of treatment with LAMOTRIGINE, the patient should be instructed that a rash or other signs or symptoms of hypersensitivity (e.g., fever, lymphadenopathy) may herald a serious medical event and that the patient should report any such occurrence to a physician immediately.

5.3 Acute Multiorgan Failure

Multiorgan failure, which in some cases has been fatal or irreversible, has been observed in patients receiving LAMOTRIGINE. Fatalities associated with multiorgan failure and various degrees of hepatic failure have been reported in 2 of 3,796 adult patients and 4 of 2,435 pediatric patients who received LAMOTRIGINE in epilepsy clinical trials. No such fatalities have been reported in bipolar patients in clinical trials. Rare fatalities from multiorgan failure have also been reported in compassionate plea and postmarketing use. The majority of these deaths occurred in association with other serious medical events, including status epilepticus and overwhelming sepsis, and hantavirus, making it difficult to identify the initial cause.

Additionally, 3 patients (a 45-year-old woman, a 3.5-year-old boy, and an 11-year-old girl) developed multiorgan dysfunction and disseminated intravascular coagulation 9 to 14 days after LAMOTRIGINE was added to their AED regimens. Rash and elevated transaminases were also present in all patients and rhabdomyolysis was noted in 2 patients. Both pediatric patients were receiving concomitant therapy with valproate, while the adult patient was being treated with carbamazepine and clonazepam. All patients subsequently recovered with supportive care after treatment with LAMOTRIGINE was discontinued.

5.4 Blood Dyscrasias

There have been reports of blood dyscrasias that may or may not be associated with the hypersensitivity syndrome. These have included neutropenia, leukopenia, anemia, thrombocytopenia, pancytopenia, and, rarely, aplastic anemia and pure red cell aplasia.

5.5 Suicidal Behavior and Ideation

Antiepileptic drugs (AEDs), including LAMOTRIGINE, increase the risk of suicidal thoughts or behavior in patients taking these drugs for any indication. Patients treated with any AED for any indication should be monitored for the emergence or worsening of depression, suicidal thoughts or behavior, and/or any unusual changes in mood or behavior.

Pooled analyses of 199 placebo-controlled clinical trials (mono- and adjunctive therapy) of 11 different AEDs showed that patients randomized to one of the AEDs had approximately twice the risk (adjusted Relative Risk 1.8, 95% CI:1.2, 2.7) of suicidal thinking or behavior compared to patients randomized to placebo. In these trials, which had a median treatment duration of 12 weeks, the estimated incidence of suicidal behavior or ideation among 27,863 AED-treated patients was 0.43%, compared to 0.24% among 16,029 placebo-treated patients, representing an increase of approximately 1 case of suicidal thinking or behavior for every 530 patients treated. There were 4 suicides in drug-treated patients in the trials and none in placebo-treated patients, but the number of events is too small to allow any conclusion about drug effect on suicide.

The increased risk of suicidal thoughts or behavior with AEDs was observed as early as 1 week after starting treatment with AEDs and persisted for the duration of treatment assessed. Because most trials included in the analysis did not extend beyond 24 weeks, the risk of suicidal thoughts or behavior beyond 24 weeks could not be assessed.

The risk of suicidal thoughts or behavior was generally consistent among drugs in the data analyzed. The finding of increased risk with AEDs of varying mechanism of action and across a range of indications suggests that the risk applies to all AEDs used for any indication. The risk did not vary substantially by age (5 to 100 years) in the clinical trials analyzed.

Table 7 shows absolute and relative risk by indication for all evaluated AEDs.

Table 7. Risk by Indication for Antiepileptic Drugs in the Pooled Analysis
Indication | Placebo Patients with Events Per 1,000 Patients | Drug Patients With Events Per 1,000 Patients | Relative Risk: Incidence of Events in Drug Patients/Incidence in Placebo Patients | Risk Difference: Additional Drug Patients With Events Per 1,000 Patients
Epilepsy | 1.0 | 3.4 | 3.5 | 2.4
Psychiatric | 5.7 | 8.5 | 1.5 | 2.9
Other | 1.0 | 1.8 | 1.9 | 0.9
Total | 2.4 | 4.3 | 1.8 | 1.9

The relative risk for suicidal thoughts or behavior was higher in clinical trials for epilepsy than in clinical trials for psychiatric or other conditions, but the absolute risk differences were similar for the epilepsy and psychiatric indications.

Anyone considering prescribing LAMOTRIGINE or any other AED must balance the risk of suicidal thoughts or behavior with the risk of untreated illness. Epilepsy and many other illnesses for which AEDs are prescribed are themselves associated with morbidity and mortality and an increased risk of suicidal thoughts and behavior. Should suicidal thoughts and behavior emerge during treatment, the prescriber needs to consider whether the emergence of these symptoms in any given patient may be related to the illness being treated.

Patients, their caregivers, and families should be informed that AEDs increase the risk of suicidal thoughts and behavior and should be advised of the need to be alert for the emergence or worsening of the signs and symptoms of depression, any unusual changes in mood or behavior, or the emergence of suicidal thoughts, behavior, or thoughts about self-harm. Behaviors of concern should be reported immediately to healthcare providers.

5.6 Use in Patients With Bipolar Disorder

Acute Treatment of Mood Episodes: Safety and effectiveness of LAMOTRIGINE in the acute treatment of mood episodes have not been established.

Children and Adolescents (less than 18 years of age): Safety and effectiveness of LAMOTRIGINE in patients below the age of 18 years with mood disorders have not been established [see Suicidal Behavior and Ideation (5.5)].

Clinical Worsening and Suicide Risk Associated With Bipolar Disorder: Patients with bipolar disorder may experience worsening of their depressive symptoms and/or the emergence of suicidal ideation and behaviors (suicidality) whether or not they are taking medications for bipolar disorder. Patients should be closely monitored for clinical worsening (including development of new symptoms) and suicidality, especially at the beginning of a course of treatment, or at the time of dose changes.

In addition, patients with a history of suicidal behavior or thoughts, those patients exhibiting a significant degree of suicidal ideation prior to commencement of treatment, and young adults are at an increased risk of suicidal thoughts or suicide attempts, and should receive careful monitoring during treatment [see Suicidal Behavior and Ideation (5.5)].

Consideration should be given to changing the therapeutic regimen, including possibly discontinuing the medication, in patients who experience clinical worsening (including development of new symptoms) and/or the emergence of suicidal ideation/behavior especially if these symptoms are severe, abrupt in onset, or were not part of the patient's presenting symptoms.

Prescriptions for LAMOTRIGINE should be written for the smallest quantity of tablets consistent with good patient management in order to reduce the risk of overdose. Overdoses have been reported for LAMOTRIGINE, some of which have been fatal [see Overdosage (10.1)].

5.7 Potential Medication Errors

Medication errors involving LAMOTRIGINE have occurred. In particular, the name LAMOTRIGINE or lamotrigine can be confused with the names of other commonly used medications. Medication errors may also occur between the different formulations of LAMOTRIGINE. To reduce the potential of medication errors, write and say LAMOTRIGINE clearly. Depictions of the LAMOTRIGINE Tablets can be found in the Medication Guide that accompanies the product to highlight the distinctive markings, colors, and shapes that serve to identify the different presentations of the drug and thus may help reduce the risk of medication errors. To avoid the medication error of using the wrong drug or formulation, patients should be strongly advised to visually inspect their tablets to verify that they are LAMOTRIGINE, as well as the correct formulation of LAMOTRIGINE, each time they fill their prescription.

5.8 Concomitant Use With Oral Contraceptives

Some estrogen-containing oral contraceptives have been shown to decrease serum concentrations of lamotrigine [see Clinical Pharmacology (12.3)]. Dosage adjustments will be necessary in most patients who start or stop estrogen-containing oral contraceptives while taking LAMOTRIGINE [see Dosage and Administration (2.1)]. During the week of inactive hormone preparation ("pill-free" week) of oral contraceptive therapy, plasma lamotrigine levels are expected to rise, as much as doubling at the end of the week. Adverse reactions consistent with elevated levels of lamotrigine, such as dizziness, ataxia, and diplopia, could occur.

5.9 Withdrawal Seizures

As with other AEDs, LAMOTRIGINE should not be abruptly discontinued. In patients with epilepsy there is a possibility of increasing seizure frequency. In clinical trials in patients with Bipolar Disorder, 2 patients experienced seizures shortly after abrupt withdrawal of LAMOTRIGINE. However, there were confounding factors that may have contributed to the occurrence of seizures in these bipolar patients. Unless safety concerns require a more rapid withdrawal, the dose of LAMOTRIGINE should be tapered over a period of at least 2 weeks (approximately 50% reduction per week) [see Dosage and Administration (2.1)].

5.10 Status Epilepticus

Valid estimates of the incidence of treatment-emergent status epilepticus among patients treated with LAMOTRIGINE are difficult to obtain because reporters participating in clinical trials did not all employ identical rules for identifying cases. At a minimum, 7 of 2,343 adult patients had episodes that could unequivocally be described as status epilepticus. In addition, a number of reports of variably defined episodes of seizure exacerbation (e.g., seizure clusters, seizure flurries, etc.) were made.

5.11 Sudden Unexplained Death in Epilepsy (SUDEP)

During the premarketing development of LAMOTRIGINE, 20 sudden and unexplained deaths were recorded among a cohort of 4,700 patients with epilepsy (5,747 patient-years of exposure).

Some of these could represent seizure-related deaths in which the seizure was not observed, e.g., at night. This represents an incidence of 0.0035 deaths per patient-year. Although this rate exceeds that expected in a healthy population matched for age and sex, it is within the range of estimates for the incidence of sudden unexplained deaths in patients with epilepsy not receiving LAMOTRIGINE (ranging from 0.0005 for the general population of patients with epilepsy, to 0.004 for a recently studied clinical trial population similar to that in the clinical development program for LAMOTRIGINE, to 0.005 for patients with refractory epilepsy). Consequently, whether these figures are reassuring or suggest concern depends on the comparability of the populations reported upon to the cohort receiving LAMOTRIGINE and the accuracy of the estimates provided. Probably most reassuring is the similarity of estimated SUDEP rates in patients receiving LAMOTRIGINE and those receiving other AEDs, chemically unrelated to each other, that underwent clinical testing in similar populations. Importantly, that drug is chemically unrelated to LAMOTRIGINE. This evidence suggests, although it certainly does not prove, that the high SUDEP rates reflect population rates, not a drug effect.

5.12 Addition of LAMOTRIGINE to a Multidrug Regimen That Includes Valproate

Because valproate reduces the clearance of lamotrigine, the dosage of lamotrigine in the presence of valproate is less than half of that required in its absence.

5.13 Binding in the Eye and Other Melanin-Containing Tissues

Because lamotrigine binds to melanin, it could accumulate in melanin-rich tissues over time. This raises the possibility that lamotrigine may cause toxicity in these tissues after extended use. Although ophthalmological testing was performed in one controlled clinical trial, the testing was inadequate to exclude subtle effects or injury occurring after long-term exposure. Moreover, the capacity of available tests to detect potentially adverse consequences, if any, of lamotrigine's binding to melanin is unknown [see Clinical Pharmacology (12.2)].

Accordingly, although there are no specific recommendations for periodic ophthalmological monitoring, prescribers should be aware of the possibility of long-term ophthalmologic effects.

5.14 Laboratory Tests

The value of monitoring plasma concentrations of lamotrigine in patients treated with LAMOTRIGINE has not been established. Because of the possible pharmacokinetic interactions between lamotrigine and other drugs including AEDs (see Table 15), monitoring of the plasma levels of lamotrigine and concomitant drugs may be indicated, particularly during dosage adjustments. In general, clinical judgment should be exercised regarding monitoring of plasma levels of lamotrigine and other drugs and whether or not dosage adjustments are necessary.

6 ADVERSE REACTIONS

The following adverse reactions are described in more detail in the Warnings and Precautions section of the label:

- Serious skin rashes [see Warnings and Precautions (5.1)]
- Hypersensitivity reactions [see Warnings and Precautions (5.2)]
- Acute multiorgan failure [see Warnings and Precautions (5.3)]
- Blood dyscrasias [see Warnings and Precautions (5.4)]
- Suicidal behavior and ideation [see Warnings and Precautions (5.5)]
- Withdrawal seizures [see Warnings and Precautions (5.9)]
- Status epilepticus [see Warnings and Precautions (5.10)]
- Sudden unexplained death in epilepsy [see Warnings and Precautions (5.11)]

6.1 Clinical Trials

Because clinical trials are conducted under widely varying conditions, adverse reaction rates observed in the clinical trials of a drug cannot be directly compared with rates in the clinical trials of another drug and may not reflect the rates observed in practice.

LAMOTRIGINE has been evaluated for safety in patients with epilepsy and in patients with Bipolar I Disorder. Adverse reactions reported for each of these patient populations are provided below. Excluded are adverse reactions considered too general to be informative and those not reasonably attributable to the use of the drug.

Epilepsy: Most Common Adverse Reactions in All Clinical Studies: Adjunctive Therapy in Adults With Epilepsy: The most commonly observed (≥5% for LAMOTRIGINE and more common on drug than placebo) adverse reactions seen in association with LAMOTRIGINE during adjunctive therapy in adults and not seen at an equivalent frequency among placebo-treated patients were: dizziness, ataxia, somnolence, headache, diplopia, blurred vision, nausea, vomiting, and rash. Dizziness, diplopia, ataxia, blurred vision, nausea, and vomiting were dose-related. Dizziness, diplopia, ataxia, and blurred vision occurred more commonly in patients receiving carbamazepine with LAMOTRIGINE than in patients receiving other AEDs with LAMOTRIGINE. Clinical data suggest a higher incidence of rash, including serious rash, in patients receiving concomitant valproate than in patients not receiving valproate [see Warnings and Precautions (5.1)].

Approximately 11% of the 3,378 adult patients who received LAMOTRIGINE as adjunctive therapy in premarketing clinical trials discontinued treatment because of an adverse reaction. The adverse reactions most commonly associated with discontinuation were rash (3.0%), dizziness (2.8%), and headache (2.5%).

In a dose-response study in adults, the rate of discontinuation of LAMOTRIGINE for dizziness, ataxia, diplopia, blurred vision, nausea, and vomiting was dose-related.

Monotherapy in Adults With Epilepsy: The most commonly observed (≥5% for LAMOTRIGINE and more common on drug than placebo) adverse reactions seen in association with the use of LAMOTRIGINE during the monotherapy phase of the controlled trial in adults not seen at an equivalent rate in the control group were vomiting, coordination abnormality, dyspepsia, nausea, dizziness, rhinitis, anxiety, insomnia, infection, pain, weight decrease, chest pain, and dysmenorrhea. The most commonly observed (≥5% for LAMOTRIGINE and more common on drug than placebo) adverse reactions associated with the use of LAMOTRIGINE during the conversion to monotherapy (add-on) period, not seen at an equivalent frequency among low-dose valproate-treated patients, were dizziness, headache, nausea, asthenia, coordination abnormality, vomiting, rash, somnolence, diplopia, ataxia, accidental injury, tremor, blurred vision, insomnia, nystagmus, diarrhea, lymphadenopathy, pruritus, and sinusitis.

Approximately 10% of the 420 adult patients who received LAMOTRIGINE as monotherapy in premarketing clinical trials discontinued treatment because of an adverse reaction. The adverse reactions most commonly associated with discontinuation were rash (4.5%), headache (3.1%), and asthenia (2.4%).

Adjunctive Therapy in Pediatric Patients With Epilepsy: The most commonly observed (≥5% for LAMOTRIGINE and more common on drug than placebo) adverse reactions seen in association with the use of LAMOTRIGINE as adjunctive treatment in pediatric patients 2 to16 years of age and not seen at an equivalent rate in the control group were infection, vomiting, rash, fever, somnolence, accidental injury, dizziness, diarrhea, abdominal pain, nausea, ataxia, tremor, asthenia, bronchitis, flu syndrome, and diplopia.

In 339 patients 2 to 16 years of age with partial seizures or generalized seizures of Lennox-Gastaut syndrome, 4.2% of patients on LAMOTRIGINE and 2.9% of patients on placebo discontinued due to adverse reactions. The most commonly reported adverse reaction that led to discontinuation of LAMOTRIGINE was rash.

Approximately 11.5% of the 1,081 pediatric patients 2 to 16 years of age who received LAMOTRIGINE as adjunctive therapy in premarketing clinical trials discontinued treatment because of an adverse reaction. The adverse reactions most commonly associated with discontinuation were rash (4.4%), reaction aggravated (1.7%), and ataxia (0.6%).

Controlled Adjunctive Clinical Studies in Adults With Epilepsy: Table 8 lists treatment-emergent adverse reactions that occurred in at least 2% of adult patients with epilepsy treated with LAMOTRIGINE in placebo-controlled trials and were numerically more common in the patients treated with LAMOTRIGINE. In these studies, either LAMOTRIGINE or placebo was added to the patient's current AED therapy. Adverse reactions were usually mild to moderate in intensity.

Table 8. Treatment-Emergent Adverse Reaction Incidence in Placebo-Controlled Adjunctive Trials in Adult Patients With Epilepsy [Patients in these adjunctive studies were receiving 1 to 3 of the following concomitant AEDs (carbamazepine, phenytoin, phenobarbital, or primidone) in addition to LAMOTRIGINE or placebo. Patients may have reported multiple adverse reactions during the study or at discontinuation; thus, patients may be included in more than one category.] (Adverse reactions in at least 2% of patients treated with LAMOTRIGINE and numerically more frequent than in the placebo group.)
Body System/ Adverse Experience | Percent of Patients Receiving Adjunctive LAMOTRIGINE (n = 711) | Percent of Patients Receiving Adjunctive Placebo (n = 419)
Body as a whole
Headache | 29 | 19
Flu syndrome | 7 | 6
Fever | 6 | 4
Abdominal pain | 5 | 4
Neck Pain | 2 | 1
Reaction aggravated (Seizure exacerbation) | 2 | 1
Digestive
Nausea | 19 | 10
Vomiting | 9 | 4
Diarrhea | 6 | 4
Dyspepsia | 5 | 2
Constipation | 4 | 3
Anorexia | 2 | 1
Musculoskeletal
Arthralgia | 2 | 0
Nervous
Dizziness | 38 | 13
Ataxia | 22 | 6
Somnolence | 14 | 7
Incoordination | 6 | 2
Insomnia | 6 | 2
Tremor | 4 | 1
Depression | 4 | 3
Anxiety | 4 | 3
Convulsion | 3 | 1
Irritability | 3 | 2
Speech disorder | 3 | 0
Concentration disturbance | 2 | 1
Respiratory
Rhinitis | 14 | 9
Pharyngitis | 10 | 9
Cough increased | 8 | 6
Skin and appendages
Rash | 10 | 5
Pruritus | 3 | 2
Special senses
Diplopia | 28 | 7
Blurred vision | 16 | 5
Vision abnormality | 3 | 1
Urogenital
Female patients only | (n = 365) | (n = 207)
Dysmenorrhea | 7 | 6
Vaginitis | 4 | 1
Amenorrhea | 2 | 1

In a randomized, parallel study comparing placebo and 300 and 500 mg/day of LAMOTRIGINE, some of the more common drug-related adverse reactions were dose-related (see Table 9).

Table 9. Dose-Related Adverse Reactions From a Randomized, Placebo-Controlled Adjunctive Trial in Adults With Epilepsy
 | Percent of Patients Experiencing Adverse Experiences
Adverse Experience | Placebo (n = 73) | LAMOTRIGINE 300 mg (n = 71) | LAMOTRIGINE 500 mg (n = 72)
Ataxia | 10 | 10 | 28 [Significantly greater than placebo group (p<0.05).] [Significantly greater than group receiving LAMOTRIGINE 300 mg (p<0.05).]
Blurred vision | 10 | 11 | 25
Diplopia | 8 | 24 | 49
Dizziness | 27 | 31 | 54
Nausea | 11 | 18 | 25
Vomiting | 4 | 11 | 18

The overall adverse reaction profile for LAMOTRIGINE was similar between females and males, and was independent of age. Because the largest non-Caucasian racial subgroup was only 6% of patients exposed to LAMOTRIGINE in placebo-controlled trials, there are insufficient data to support a statement regarding the distribution of adverse reaction reports by race. Generally, females receiving either LAMOTRIGINE as adjunctive therapy or placebo were more likely to report adverse reactions than males. The only adverse reaction for which the reports on LAMOTRIGINE were greater than 10% more frequent in females than males (without a corresponding difference by gender on placebo) was dizziness (difference = 16.5%). There was little difference between females and males in the rates of discontinuation of LAMOTRIGINE for individual adverse reactions.

Controlled Monotherapy Trial in Adults With Partial Seizures: Table 10 lists treatment-emergent adverse reactions that occurred in at least 5% of patients with epilepsy treated with monotherapy with LAMOTRIGINE in a double-blind trial following discontinuation of either concomitant carbamazepine or phenytoin not seen at an equivalent frequency in the control group.

Table 10. Treatment-Emergent Adverse Reaction Incidence in Adults With Partial Seizures in a Controlled Monotherapy Trial [Patients in these studies were converted to LAMOTRIGINE or valproate monotherapy from adjunctive therapy with carbamazepine or phenytoin. Patients may have reported multiple adverse reactions during the study; thus, patients may be included in more than one category.] (Adverse reactions in at least 5% of patients treated with LAMOTRIGINE and numerically more frequent than in the valproate group.)
Body System/ Adverse Experience | Percent of Patients Receiving LAMOTRIGINE as Monotherapy [Up to 500 mg/day.] (n = 43) | Percent of Patients Receiving Low-Dose Valproate [1,000 mg/day.] Monotherapy (n = 44)
Body as a whole
Pain | 5 | 0
Infection | 5 | 2
Chest pain | 5 | 2
Digestive
Vomiting | 9 | 0
Dyspepsia | 7 | 2
Nausea | 7 | 2
Metabolic and nutritional
Weight decrease | 5 | 2
Nervous
Coordination abnormality | 7 | 0
Dizziness | 7 | 0
Anxiety | 5 | 0
Insomnia | 5 | 2
Respiratory
Rhinitis | 7 | 2
Urogenital (female patients only) | (n = 21) | (n = 28)
Dysmenorrhea | 5 | 0

Adverse reactions that occurred with a frequency of less than 5% and greater than 2% of patients receiving LAMOTRIGINE and numerically more frequent than placebo were:
Body as a Whole: Asthenia, fever.
Digestive: Anorexia, dry mouth, rectal hemorrhage, peptic ulcer.
Metabolic and Nutritional: Peripheral edema.
Nervous System: Amnesia, ataxia, depression, hypesthesia, libido increase, decreased reflexes, increased reflexes, nystagmus, irritability, suicidal ideation.
Respiratory: Epistaxis, bronchitis, dyspnea.
Skin and Appendages: Contact dermatitis, dry skin, sweating.
Special Senses: Vision abnormality.

Incidence in Controlled Adjunctive Trials in Pediatric Patients With Epilepsy: Table 11 lists adverse reactions that occurred in at least 2% of 339 pediatric patients with partial seizures or generalized seizures of Lennox-Gastaut syndrome, who received LAMOTRIGINE up to 15 mg/kg/day or a maximum of 750 mg/day. Reported adverse reactions were classified using COSTART terminology.

Table 11. Treatment-Emergent Adverse Reaction Incidence in Placebo-Controlled Adjunctive Trials in Pediatric Patients With Epilepsy (Adverse reactions in at least 2% of patients treated with LAMOTRIGINE and numerically more frequent than in the placebo group.)
Body System/ Adverse Experience | Percent of Patients Receiving LAMOTRIGINE (n = 168) | Percent of Patients Receiving Placebo (n = 171)
Body as a whole
Infection | 20 | 17
Fever | 15 | 14
Accidental injury | 14 | 12
Abdominal pain | 10 | 5
Asthenia | 8 | 4
Flu syndrome | 7 | 6
Pain | 5 | 4
Facial edema | 2 | 1
Photosensitivity | 2 | 0
Cardiovascular
Hemorrhage | 2 | 1
Digestive
Vomiting | 20 | 16
Diarrhea | 11 | 9
Nausea | 10 | 2
Constipation | 4 | 2
Dyspepsia | 2 | 1
Hemic and lymphatic
Lymphadenopathy | 2 | 1
Metabolic and nutritional
Edema | 2 | 0
Nervous system
Somnolence | 17 | 15
Dizziness | 14 | 4
Ataxia | 11 | 3
Tremor | 10 | 1
Emotional lability | 4 | 2
Gait abnormality | 4 | 2
Thinking abnormality | 3 | 2
Convulsions | 2 | 1
Nervousness | 2 | 1
Vertigo | 2 | 1
Respiratory
Pharyngitis | 14 | 11
Bronchitis | 7 | 5
Increased cough | 7 | 6
Sinusitis | 2 | 1
Bronchospasm | 2 | 1
Skin
Rash | 14 | 12
Eczema | 2 | 1
Pruritus | 2 | 1
Special senses
Diplopia | 5 | 1
Blurred vision | 4 | 1
Visual abnormality | 2 | 0
Urogenital
Male and female patients
Urinary tract infection | 3 | 0

Bipolar Disorder: The most commonly observed (≥5%) treatment-emergent adverse reactions seen in association with the use of LAMOTRIGINE as monotherapy (100 to 400 mg/day) in adult patients (≥18 years of age) with Bipolar Disorder in the 2 double-blind, placebo-controlled trials of 18 months' duration, and numerically more frequent than in placebo-treated patients are included in Table 12. Adverse reactions that occurred in at least 5% of patients and were numerically more common during the dose-escalation phase of LAMOTRIGINE in these trials (when patients may have been receiving concomitant medications) compared with the monotherapy phase were: headache (25%), rash (11%), dizziness (10%), diarrhea (8%), dream abnormality (6%), and pruritus (6%).

During the monotherapy phase of the double-blind, placebo-controlled trials of 18 months' duration, 13% of 227 patients who received LAMOTRIGINE (100 to 400 mg/day), 16% of 190 patients who received placebo, and 23% of 166 patients who received lithium discontinued therapy because of an adverse reaction. The adverse reactions which most commonly led to discontinuation of LAMOTRIGINE were rash (3%) and mania/hypomania/mixed mood adverse reactions (2%). Approximately 16% of 2,401 patients who received LAMOTRIGINE (50 to 500 mg/day) for Bipolar Disorder in premarketing trials discontinued therapy because of an adverse reaction; most commonly due to rash (5%) and mania/hypomania/mixed mood adverse reactions (2%).

The overall adverse reaction profile for LAMOTRIGINE was similar between females and males, between elderly and nonelderly patients, and among racial groups.

Table 12. Treatment-Emergent Adverse Reaction Incidence in 2 Placebo-Controlled Trials in Adults With Bipolar I Disorder* (Adverse reactions in at least 5% of patients treated with LAMOTRIGINE as monotherapy and numerically more frequent than in the placebo group.)
Body System/ Adverse Experience | Percent of Patients Receiving LAMOTRIGINE (n = 227) | Percent of Patients Receiving Placebo (n = 190)
General
Back pain | 8 | 6
Fatigue | 8 | 5
Abdominal Pain | 6 | 3
Digestive
Nausea | 14 | 11
Constipation | 5 | 2
Vomiting | 5 | 2
Nervous System
Insomnia | 10 | 6
Somnolence | 9 | 7
Xerostomia (dry mouth) | 6 | 4
Respiratory
Rhinitis | 7 | 4
Exacerbation of cough | 5 | 3
Pharyngitis | 5 | 4
Skin
Rash (nonserious)† | 7 | 5

Patients in these studies were converted to LAMOTRIGINE (100 to 400 mg/day) or placebo monotherapy from add-on therapy with other psychotropic medications. Patients may have reported multiple adverse reactions during the study; thus, patients may be included in more than one category.

In the overall bipolar and other mood disorders clinical trials, the rate of serious rash was 0.08% (1 of 1,233) of adult patients who received LAMOTRIGINE as initial monotherapy and 0.13% (2 of 1,538) of adult patients who received LAMOTRIGINE as adjunctive therapy [see Warnings and Precautions (5.1)].

These adverse reactions were usually mild to moderate in intensity. Other reactions that occurred in 5% or more patients but equally or more frequently in the placebo group included: dizziness, mania, headache, infection, influenza, pain, accidental injury, diarrhea, and dyspepsia.

Adverse reactions that occurred with a frequency of less than 5% and greater than 1% of patients receiving LAMOTRIGINE and numerically more frequent than placebo were:

General: Fever, neck pain.
  Cardiovascular: Migraine.
  Digestive: Flatulence
  Metabolic and Nutritional: Weight gain, edema.
  Musculoskeletal: Arthralgia, myalgia.
  Nervous System: Amnesia, depression, agitation, emotional lability, dyspraxia, abnormal thoughts, dream abnormality, hypoesthesia.
  Respiratory: Sinusitis.
  Urogenital: Urinary frequency.

Adverse Reactions Following Abrupt Discontinuation: In the 2 maintenance trials, there was no increase in the incidence, severity or type of adverse reactions in Bipolar Disorder patients after abruptly terminating therapy with LAMOTRIGINE. In clinical trials in patients with Bipolar Disorder, 2 patients experienced seizures shortly after abrupt withdrawal of LAMOTRIGINE. However, there were confounding factors that may have contributed to the occurrence of seizures in these bipolar patients [see Warnings and Precautions (5.9)].

Mania/Hypomania/Mixed Episodes: During the double-blind, placebo-controlled clinical trials in Bipolar I Disorder in which patients were converted to monotherapy with LAMOTRIGINE (100 to 400 mg/day) from other psychotropic medications and followed for up to 18 months, the rates of manic or hypomanic or mixed mood episodes reported as adverse reactions were 5% for patients treated with LAMOTRIGINE (n = 227), 4% for patients treated with lithium (n = 166), and 7% for patients treated with placebo (n = 190). In all bipolar controlled trials combined, adverse reactions of mania (including hypomania and mixed mood episodes) were reported in 5% of patients treated with LAMOTRIGINE (n = 956), 3% of patients treated with lithium (n = 280), and 4% of patients treated with placebo (n = 803).

6.2 Other Adverse Reactions Observed in All Clinical Trials

LAMOTRIGINE has been administered to 6,694 individuals for whom complete adverse reaction data was captured during all clinical trials, only some of which were placebo controlled. During these trials, all adverse reactions were recorded by the clinical investigators using terminology of their own choosing. To provide a meaningful estimate of the proportion of individuals having adverse reactions, similar types of adverse reactions were grouped into a smaller number of standardized categories using modified COSTART dictionary terminology. The frequencies presented represent the proportion of the 6,694 individuals exposed to LAMOTRIGINE who experienced an event of the type cited on at least one occasion while receiving LAMOTRIGINE. All reported adverse reactions are included except those already listed in the previous tables or elsewhere in the labeling, those too general to be informative, and those not reasonably associated with the use of the drug.

Adverse reactions are further classified within body system categories and enumerated in order of decreasing frequency using the following definitions: frequent adverse reactions are defined as those occurring in at least 1/100 patients; infrequent adverse reactions are those occurring in 1/100 to 1/1,000 patients; rare adverse reactions are those occurring in fewer than 1/1,000 patients.

Body as a Whole: Infrequent: Allergic reaction, chills, and malaise.

Cardiovascular System: Infrequent: Flushing, hot flashes, hypertension, palpitations, postural hypotension, syncope, tachycardia, and vasodilation.

Dermatological: Infrequent: Acne, alopecia, hirsutism, maculopapular rash, skin discoloration, and urticaria. Rare: Angioedema, erythema, exfoliative dermatitis, fungal dermatitis, herpes zoster, leukoderma, multiforme erythema, petechial rash, pustular rash, Stevens-Johnson syndrome, and vesiculobullous rash.

Digestive System: Infrequent: Dysphagia, eructation, gastritis, gingivitis, increased appetite, increased salivation, liver function tests abnormal, and mouth ulceration. Rare: Gastrointestinal hemorrhage, glossitis, gum hemorrhage, gum hyperplasia, hematemesis, hemorrhagic colitis, hepatitis, melena, stomach ulcer, stomatitis, and tongue edema.

Endocrine System: Rare: Goiter and hypothyroidism.

Hematologic and Lymphatic System: Infrequent: Ecchymosis and leukopenia. Rare: Anemia, eosinophilia, fibrin decrease, fibrinogen decrease, iron deficiency anemia, leukocytosis, lymphocytosis, macrocytic anemia, petechia, and thrombocytopenia.

Metabolic and Nutritional Disorders: Infrequent: Aspartate transaminase increased. Rare: Alcohol intolerance, alkaline phosphatase increase, alanine transaminase increase, bilirubinemia, general edema, gamma glutamyl transpeptidase increase, and hyperglycemia.

Musculoskeletal System: Infrequent: Arthritis, leg cramps, myasthenia, and twitching. Rare: Bursitis, muscle atrophy, pathological fracture, and tendinous contracture.

Nervous System: Frequent: Confusion and paresthesia. Infrequent: Akathisia, apathy, aphasia, CNS depression, depersonalization, dysarthria, dyskinesia, euphoria, hallucinations, hostility, hyperkinesia, hypertonia, libido decreased, memory decrease, mind racing, movement disorder, myoclonus, panic attack, paranoid reaction, personality disorder, psychosis, sleep disorder, stupor, and suicidal ideation. Rare: Choreoathetosis, delirium, delusions, dysphoria, dystonia, extrapyramidal syndrome, faintness, grand mal convulsions, hemiplegia, hyperalgesia, hyperesthesia, hypokinesia, hypotonia, manic depression reaction, muscle spasm, neuralgia, neurosis, paralysis, and peripheral neuritis.

Respiratory System: Infrequent: Yawn. Rare: Hiccup and hyperventilation.

Special Senses: Frequent: Amblyopia. Infrequent: Abnormality of accommodation, conjunctivitis, dry eyes, ear pain, photophobia, taste perversion, and tinnitus. Rare: Deafness, lacrimation disorder, oscillopsia, parosmia, ptosis, strabismus, taste loss, uveitis, and visual field defect.

Urogenital System: Infrequent: Abnormal ejaculation, hematuria, impotence, menorrhagia, polyuria, and urinary incontinence. Rare: Acute kidney failure, anorgasmia, breast abscess, breast neoplasm, creatinine increase, cystitis, dysuria, epididymitis, female lactation, kidney failure, kidney pain, nocturia, urinary retention, and urinary urgency.

6.3 Postmarketing Experience

The following adverse events (not listed above in clinical trials or other sections of the prescribing information) have been identified during postapproval use of LAMOTRIGINE. Because these events are reported voluntarily from a population of uncertain size, it is not always possible to reliably estimate their frequency or establish a causal relationship to drug exposure.

Blood and Lymphatic: Agranulocytosis, hemolytic anemia.
Gastrointestinal: Esophagitis.
Hepatobiliary Tract and Pancreas: Pancreatitis.
Immunologic: Lupus-like reaction, vasculitis.
Lower Respiratory: Apnea.
Musculoskeletal: Rhabdomyolysis has been observed in patients experiencing hypersensitivity reactions.
Neurology: Exacerbation of Parkinsonian symptoms in patients with pre-existing Parkinson's disease, tics.
Non-site Specific: Progressive immunosuppression.

7 DRUG INTERACTIONS

Significant drug interactions with lamotrigine are summarized in Table 13. Additional details of these drug interaction studies are provided in the Clinical Pharmacology subsection [see Clinical Pharmacology (12.3)].

Table 13. Established and Other Potentially Significant Drug Interactions
Concomitant Drug | Effect on Concentration of Lamotrigine or Concomitant Drug | Clinical Comment
Estrogen-containing oral contraceptive preparation containing 30 mcg ethinylestradiol and 150 mcg levonorgestrel | ↓ lamotrigine | Decreased lamotrigine levels approximately 50%.
Estrogen-containing oral contraceptive preparation containing 30 mcg ethinylestradiol and 150 mcg levonorgestrel | ↓ levonorgestrel | Decrease in levonorgestrel component by 19%.
Carbamazepine (CBZ) and CBZ epoxide | ↓ lamotrigine | Addition of carbamazepine decreases lamotrigine concentration approximately 40%.
Carbamazepine (CBZ) and CBZ epoxide | ? CBZ epoxide | May increase CBZ epoxide levels
Phenobarbital/Primidone | ↓ lamotrigine | Decreased lamotrigine concentration approximately 40%.
Phenytoin (PHT) | ↓ lamotrigine | Decreased lamotrigine concentration approximately 40%.
Rifampin | ↓ lamotrigine | Decreased lamotrigine AUC approximately 40%.
Valproate | ↑ lamotrigine | Increased lamotrigine concentrations slightly more than 2-fold.
Valproate | ? valproate | Decreased valproate concentrations an average of 25% over a 3-week period then stabilized in healthy volunteers; no change in controlled clinical trials in epilepsy patients.
↓= Decreased (induces lamotrigine gluronidation).
↑= Increased (inhibits lamotrigine glucuronidation).
?= Conflicting data.

8 USE IN SPECIFIC POPULATIONS

8.1 Pregnancy

TERATOGENIC EFFECTS

Teratogenic Effects: Pregnancy Category C. No evidence of teratogenicity was found in mice, rats, or rabbits when lamotrigine was orally administered to pregnant animals during the period of organogenesis at doses up to 1.2, 0.5, and 1.1 times, respectively, on a mg/m^2 basis, the highest usual human maintenance dose (i.e., 500 mg/day). However, maternal toxicity and secondary fetal toxicity producing reduced fetal weight and/or delayed ossification were seen in mice and rats, but not in rabbits at these doses. Teratology studies were also conducted using bolus intravenous administration of the isethionate salt of lamotrigine in rats and rabbits. In rat dams administered an intravenous dose at 0.6 times the highest usual human maintenance dose, the incidence of intrauterine death without signs of teratogenicity was increased.

A behavioral teratology study was conducted in rats dosed during the period of organogenesis. At day 21 postpartum, offspring of dams receiving 5 mg/kg/day or higher displayed a significantly longer latent period for open field exploration and a lower frequency of rearing. In a swimming maze test performed on days 39 to 44 postpartum, time to completion was increased in offspring of dams receiving 25 mg/kg/day. These doses represent 0.1 and 0.5 times the clinical dose on a mg/m^2 basis, respectively.

Lamotrigine did not affect fertility, teratogenesis, or postnatal development when rats were dosed prior to and during mating, and throughout gestation and lactation at doses equivalent to 0.4 times the highest usual human maintenance dose on a mg/m^2 basis.

When pregnant rats were orally dosed at 0.1, 0.14, or 0.3 times the highest human maintenance dose (on a mg/m^2 basis) during the latter part of gestation (days 15 to 20), maternal toxicity and fetal death were seen. In dams, food consumption and weight gain were reduced, and the gestation period was slightly prolonged (22.6 vs. 22.0 days in the control group). Stillborn pups were found in all 3 drug-treated groups with the highest number in the high-dose group. Postnatal death was also seen, but only in the 2 highest doses, and occurred between days 1 and 20. Some of these deaths appear to be drug-related and not secondary to the maternal toxicity. A no-observed-effect level (NOEL) could not be determined for this study.

Although lamotrigine was not found to be teratogenic in the above studies, lamotrigine decreases fetal folate concentrations in rats, an effect known to be associated with teratogenesis in animals and humans. There are no adequate and well-controlled studies in pregnant women. Because animal reproduction studies are not always predictive of human response, this drug should be used during pregnancy only if the potential benefit justifies the potential risk to the fetus.

NONTERATOGENIC EFFECTS

Non-Teratogenic Effects: As with other AEDs, physiological changes during pregnancy may affect lamotrigine concentrations and/or therapeutic effect. There have been reports of decreased lamotrigine concentrations during pregnancy and restoration of pre-partum concentrations after delivery. Dosage adjustments may be necessary to maintain clinical response.

Pregnancy Exposure Registry:

To provide information regarding the effects of in utero exposure to LAMOTRIGINE, physicians are advised to recommend that pregnant patients taking LAMOTRIGINE enroll in the North American Antiepileptic Drug (NAAED) Pregnancy Registry. This can be done by calling the toll free number 1-888-233-2334, and must be done by patients themselves. Information on the registry can also be found at the website http://www.aedpregnancyregistry.org/.

Physicians are also encouraged to register patients in the Lamotrigine Pregnancy Registry; enrollment in this registry must be done prior to any prenatal diagnostic tests and before fetal outcome is known. Physicians can obtain information by calling the Lamotrigine Pregnancy Registry at 1-800-336-2176 (toll-free).

8.2 Labor and Delivery

The effect of LAMOTRIGINE on labor and delivery in humans is unknown.

8.3 Nursing Mothers

Preliminary data indicate that lamotrigine passes into human milk. Because the effects on the infant exposed to lamotrigine by this route are unknown, breastfeeding while taking LAMOTRIGINE is not recommended.

8.4 Pediatric Use

LAMOTRIGINE is indicated for adjunctive therapy in patients ≥2 years of age for partial seizures, and the generalized seizures of Lennox-Gastaut syndrome.

Safety and efficacy of LAMOTRIGINE, used as adjunctive treatment for partial seizures, were not demonstrated in a small randomized, double-blind, placebo-controlled, withdrawal study in very young pediatric patients (1 to 24 months). LAMOTRIGINE was associated with an increased risk for infectious adverse reactions (LAMOTRIGINE 37%, Placebo 5%), and respiratory adverse reactions (LAMOTRIGINE 26%, Placebo 5%). Infectious adverse reactions included: bronchiolitis, bronchitis, ear infection, eye infection, otitis externa, pharyngitis, urinary tract infection, and viral infection. Respiratory adverse reactions included nasal congestion, cough, and apnea.

Safety and effectiveness in patients below the age of 18 years with Bipolar Disorder has not been established.

8.5 Geriatric Use

Clinical studies of LAMOTRIGINE for epilepsy and in Bipolar Disorder did not include sufficient numbers of subjects 65 years of age and over to determine whether they respond differently from younger subjects or exhibit a different safety profile than that of younger patients. In general, dose selection for an elderly patient should be cautious, usually starting at the low end of the dosing range, reflecting the greater frequency of decreased hepatic, renal, or cardiac function, and of concomitant disease or other drug therapy.

8.6 Patients With Hepatic Impairment

Experience in patients with hepatic impairment is limited. Based on a clinical pharmacology study in 24 patients with mild, moderate, and severe liver impairment [see Clinical Pharmacology (12.3)], the following general recommendations can be made. No dosage adjustment is needed in patients with mild liver impairment. Initial, escalation, and maintenance doses should generally be reduced by approximately 25% in patients with moderate and severe liver impairment without ascites and 50% in patients with severe liver impairment with ascites. Escalation and maintenance doses may be adjusted according to clinical response [see Dosage and Administration (2.1)].

8.7 Patients With Renal Impairment

Lamotrigine is metabolized mainly by glucuronic acid conjugation, with the majority of the metabolites being recovered in the urine. In a small study comparing a single dose of lamotrigine in patients with varying degrees of renal impairment with healthy volunteers, the plasma half-life of lamotrigine was significantly longer in the patients with renal impairment [see Clinical Pharmacology (12.3)].

Initial doses of LAMOTRIGINE should be based on patients' AED regimen; reduced maintenance doses may be effective for patients with significant renal impairment. Few patients with severe renal impairment have been evaluated during chronic treatment with LAMOTRIGINE. Because there is inadequate experience in this population, LAMOTRIGINE should be used with caution in these patients [see Dosage and Administration (2.1)].

10 OVERDOSAGE

10.1 Human Overdose Experience

Overdoses involving quantities up to 15 g have been reported for LAMOTRIGINE, some of which have been fatal. Overdose has resulted in ataxia, nystagmus, increased seizures, decreased level of consciousness, coma, and intraventricular conduction delay.

10.2 Management of Overdose

There are no specific antidotes for lamotrigine. Following a suspected overdose, hospitalization of the patient is advised. General supportive care is indicated, including frequent monitoring of vital signs and close observation of the patient. If indicated, emesis should be induced or gastric lavage should be performed; usual precautions should be taken to protect the airway. It should be kept in mind that lamotrigine is rapidly absorbed [see Clinical Pharmacology (12.3)]. It is uncertain whether hemodialysis is an effective means of removing lamotrigine from the blood. In 6 renal failure patients, about 20% of the amount of lamotrigine in the body was removed by hemodialysis during a 4-hour session. A Poison Control Center should be contacted for information on the management of overdosage of LAMOTRIGINE.

11 DESCRIPTION

LAMOTRIGINE (lamotrigine), an AED of the phenyltriazine class, is chemically unrelated to existing AEDs. Its chemical name is 3,5-diamino-6-(2,3-dichlorophenyl)-as-triazine, its molecular formula is C9H7N5Cl2, and its molecular weight is 256.09. Lamotrigine is a white to pale cream-colored powder and has a pKa of 5.7. Lamotrigine is very slightly soluble in water (0.17 mg/mL at 25°C) and slightly soluble in 0.1 M HCl (4.1 mg/mL at 25°C). The structural formula is:

Lamotrigine Tablets are supplied for oral administration as 25 mg (white), 100 mg (light peach), 150 mg (cream), and 200 mg (light blue) tablets. Each tablet contains the labeled amount of lamotrigine and the following inactive ingredients: croscarmellose sodium, crospovidone, FD&C Blue #2 Aluminum Lake (200 mg strength only), FD&C Yellow No. 6 Lake (100 mg strength only), lactose monohydrate, magnesium stearate, microcrystalline cellulose, povidone, and yellow iron oxide (150 mg strength only).

12 CLINICAL PHARMACOLOGY

12.1 Mechanism of Action

The precise mechanism(s) by which lamotrigine exerts its anticonvulsant action are unknown. In animal models designed to detect anticonvulsant activity, lamotrigine was effective in preventing seizure spread in the maximum electroshock (MES) and pentylenetetrazol (scMet) tests, and prevented seizures in the visually and electrically evoked after-discharge (EEAD) tests for antiepileptic activity. Lamotrigine also displayed inhibitory properties in the kindling model in rats both during kindling development and in the fully kindled state. The relevance of these models to human epilepsy, however, is not known.

One proposed mechanism of action of lamotrigine, the relevance of which remains to be established in humans, involves an effect on sodium channels. In vitro pharmacological studies suggest that lamotrigine inhibits voltage-sensitive sodium channels, thereby stabilizing neuronal membranes and consequently modulating presynaptic transmitter release of excitatory amino acids (e.g., glutamate and aspartate).

Although the relevance for human use is unknown, the following data characterize the performance of lamotrigine in receptor binding assays. Lamotrigine had a weak inhibitory effect on the serotonin 5-HT3 receptor (IC50 = 18 μM). It does not exhibit high affinity binding (IC50>100 μM) to the following neurotransmitter receptors: adenosine A1 and A2; adrenergic α1, α2, and β; dopamine D1 and D2; γ-aminobutyric acid (GABA) A and B; histamine H1; kappa opioid; muscarinic acetylcholine; and serotonin 5-HT2. Studies have failed to detect an effect of lamotrigine on dihydropyridine-sensitive calcium channels. It had weak effects at sigma opioid receptors (IC50 = 145 μM). Lamotrigine did not inhibit the uptake of norepinephrine, dopamine, or serotonin, (IC50>200 μM) when tested in rat synaptosomes and/or human platelets in vitro.

Effect of Lamotrigine on N-Methyl d-Aspartate-Receptor Mediated Activity: Lamotrigine did not inhibit N-methyl d-aspartate (NMDA)-induced depolarizations in rat cortical slices or NMDA-induced cyclic GMP formation in immature rat cerebellum, nor did lamotrigine displace compounds that are either competitive or noncompetitive ligands at this glutamate receptor complex (CNQX, CGS, TCHP). The IC50 for lamotrigine effects on NMDA-induced currents (in the presence of 3 μM of glycine) in cultured hippocampal neurons exceeded 100 μM.

The mechanisms by which lamotrigine exerts its therapeutic action in Bipolar Disorder have not been established.

12.2 Pharmacodynamics

Folate Metabolism: In vitro, lamotrigine inhibited dihydrofolate reductase, the enzyme that catalyzes the reduction of dihydrofolate to tetrahydrofolate. Inhibition of this enzyme may interfere with the biosynthesis of nucleic acids and proteins. When oral daily doses of lamotrigine were given to pregnant rats during organogenesis, fetal, placental, and maternal folate concentrations were reduced. Significantly reduced concentrations of folate are associated with teratogenesis [see Use in Specific Populations (8.1)]. Folate concentrations were also reduced in male rats given repeated oral doses of lamotrigine. Reduced concentrations were partially returned to normal when supplemented with folinic acid.

Accumulation in Kidneys: Lamotrigine accumulated in the kidney of the male rat, causing chronic progressive nephrosis, necrosis, and mineralization. These findings are attributed to α-2 microglobulin, a species- and sex-specific protein that has not been detected in humans or other animal species.

Melanin Binding: Lamotrigine binds to melanin-containing tissues, e.g., in the eye and pigmented skin. It has been found in the uveal tract up to 52 weeks after a single dose in rodents.

Cardiovascular: In dogs, lamotrigine is extensively metabolized to a 2-N-methyl metabolite. This metabolite causes dose-dependent prolongations of the PR interval, widening of the QRS complex, and, at higher doses, complete AV conduction block. Similar cardiovascular effects are not anticipated in humans because only trace amounts of the 2-N-methyl metabolite (<0.6% of lamotrigine dose) have been found in human urine [see Clinical Pharmacology (12.3)]. However, it is conceivable that plasma concentrations of this metabolite could be increased in patients with a reduced capacity to glucuronidate lamotrigine (e.g., in patients with liver disease).

12.3 Pharmacokinetics

The pharmacokinetics of lamotrigine have been studied in patients with epilepsy, healthy young and elderly volunteers, and volunteers with chronic renal failure. Lamotrigine pharmacokinetic parameters for adult and pediatric patients and healthy normal volunteers are summarized in Tables 14 and 16.

Table 14. Mean [The majority of parameter means determined in each study had coefficients of variation between 20% and 40% for half-life and Cl/F and between 30% and 70% for Tmax. The overall mean values were calculated from individual study means that were weighted based on the number of volunteers/patients in each study. The numbers in parentheses below each parameter mean represent the range of individual volunteer/patient values across studies.] Pharmacokinetic Parameters in Healthy Volunteers and Adult Patients With Epilepsy
Adult Study Population | Number of Subjects | Tmax: Time of Maximum Plasma Concentration (hr) | t½: Elimination Half-life (hr) | Cl/F: Apparent Plasma Clearance (mL/min/kg)
Healthy volunteers taking no other medications:
Single-dose LAMOTRIGINE | 179 | 2.2 (0.25-12.0) | 32.8 (14.0-103.0) | 0.44 (0.12-1.10)
Multiple-dose LAMOTRIGINE | 36 | 1.7 (0.5-4.0) | 25.4 (11.6-61.6) | 0.58 (0.24-1.15)
Healthy volunteers taking valproate:
Single-dose LAMOTRIGINE | 6 | 1.8 (1.0-4.0) | 48.3 (31.5-88.6) | 0.30 (0.14-0.42)
Multiple-dose LAMOTRIGINE | 18 | 1.9 (0.5-3.5) | 70.3 (41.9-113.5) | 0.18 (0.12-0.33)
Patients with epilepsy taking valproate only:
Single-dose LAMOTRIGINE | 4 | 4.8 (1.8-8.4) | 58.8 (30.5-88.8) | 0.28 (0.16-0.40)
Patients with epilepsy taking carbamazepine, phenytoin, phenobarbital, or primidone [Carbamazepine, phenobarbital, phenytoin, and primidone have been shown to increase the apparent clearance of lamotrigine. Estrogen-containing oral contraceptives and rifampin have also been shown to increase the apparent clearance of lamotrigine [see Drug Interactions (7)].] plus valproate:
Single-dose LAMOTRIGINE | 25 | 3.8 (1.0-10.0) | 27.2 (11.2-51.6) | 0.53 (0.27-1.04)
Patients with epilepsy taking carbamazepine, phenytoin, phenobarbital, or primidone:
Single-dose LAMOTRIGINE | 24 | 2.3 (0.5-5.0) | 14.4 (6.4-30.4) | 1.10 (0.51-2.22)
Multiple-dose LAMOTRIGINE | 17 | 2.0 (0.75-5.93) | 12.6 (7.5-23.1) | 1.21 (0.66-1.82)

Absorption: Lamotrigine is rapidly and completely absorbed after oral administration with negligible first-pass metabolism (absolute bioavailability is 98%). The bioavailability is not affected by food. Peak plasma concentrations occur anywhere from 1.4 to 4.8 hours following drug administration. The lamotrigine chewable/dispersible tablets were found to be equivalent, whether they were administered as dispersed in water, chewed and swallowed, or swallowed as whole, to the lamotrigine compressed tablets in terms of rate and extent of absorption. In terms of rate and extent of absorption, lamotrigine orally disintegrating tablets whether disintegrated in the mouth or swallowed whole with water were equivalent to the lamotrigine compressed tablets swallowed with water.

Dose Proportionality: In healthy volunteers not receiving any other medications and given single doses, the plasma concentrations of lamotrigine increased in direct proportion to the dose administered over the range of 50 to 400 mg. In 2 small studies (n = 7 and 8) of patients with epilepsy who were maintained on other AEDs, there also was a linear relationship between dose and lamotrigine plasma concentrations at steady state following doses of 50 to 350 mg twice daily.

Distribution: Estimates of the mean apparent volume of distribution (Vd/F) of lamotrigine following oral administration ranged from 0.9 to 1.3 L/kg. Vd/F is independent of dose and is similar following single and multiple doses in both patients with epilepsy and in healthy volunteers.

Protein Binding: Data from in vitro studies indicate that lamotrigine is approximately 55% bound to human plasma proteins at plasma lamotrigine concentrations from 1 to 10 mcg/mL (10 mcg/mL is 4 to 6 times the trough plasma concentration observed in the controlled efficacy trials). Because lamotrigine is not highly bound to plasma proteins, clinically significant interactions with other drugs through competition for protein binding sites are unlikely. The binding of lamotrigine to plasma proteins did not change in the presence of therapeutic concentrations of phenytoin, phenobarbital, or valproate. Lamotrigine did not displace other AEDs (carbamazepine, phenytoin, phenobarbital) from protein binding sites.

Metabolism: Lamotrigine is metabolized predominantly by glucuronic acid conjugation; the major metabolite is an inactive 2-N-glucuronide conjugate. After oral administration of 240 mg of ^14C-lamotrigine (15 μCi) to 6 healthy volunteers, 94% was recovered in the urine and 2% was recovered in the feces. The radioactivity in the urine consisted of unchanged lamotrigine (10%), the 2-N-glucuronide (76%), a 5-N-glucuronide (10%), a 2-N-methyl metabolite (0.14%), and other unidentified minor metabolites (4%).

Enzyme Induction: The effects of lamotrigine on the induction of specific families of mixed-function oxidase isozymes have not been systematically evaluated.

Following multiple administrations (150 mg twice daily) to normal volunteers taking no other medications, lamotrigine induced its own metabolism, resulting in a 25% decrease in t½ and a 37% increase in Cl/F at steady state compared with values obtained in the same volunteers following a single dose. Evidence gathered from other sources suggests that self-induction by lamotrigine may not occur when lamotrigine is given as adjunctive therapy in patients receiving carbamazepine, phenytoin, phenobarbital, primidone, or rifampin.

Elimination: The elimination half-life and apparent clearance of lamotrigine following administration of LAMOTRIGINE to adult patients with epilepsy and healthy volunteers is summarized in Table 14. Half-life and apparent oral clearance vary depending on concomitant AEDs.

Drug Interactions: The apparent clearance of lamotrigine is affected by the coadministration of certain medications [see Warnings and Precautions (5.8, 5.12), Drug Interactions (7)].

The net effects of drug interactions with LAMOTRIGINE are summarized in Tables 13 and 15, followed by details of the drug interaction studies below.

Table 15. Summary of Drug Interactions With LAMOTRIGINE
Drug | Drug Plasma Concentration With Adjunctive LAMOTRIGINE [From adjunctive clinical trials and volunteer studies.] | Lamotrigine Plasma Concentration With Adjunctive Drugs [Net effects were estimated by comparing the mean clearance values obtained in adjunctive clinical trials and volunteers studies.]
Oral contraceptives (e.g., ethinylestradiol/levonorgestrel) [The effect of other hormonal contraceptive preparations or hormone replacement therapy on the pharmacokinetics of lamotrigine has not been systematically evaluated in clinical trials, although the effect may be similar to that seen with the ethinylestradiol/levonorgestrel combinations.] | ↔ [Modest decrease in levonorgestrel.] | ↓
Bupropion | Not assessed | ↔
Carbamazepine (CBZ) | ↔ | ↓
CBZ epoxide [Not administered, but an active metabolite of carbamazepine.] | ?
Felbamate | Not assessed | ↔
Gabapentin | Not assessed | ↔
Levetiracetam | ↔ | ↔
Lithium | ↔ | Not assessed
Olanzapine | ↔ | ↔ [Slight decrease, not expected to be clinically relevant.]
Oxcarbazepine | ↔ | ↔
10-monohydroxy oxcarbazepine metabolite [Not administered, but an active metabolite of oxcarbazepine.] | ↔
Phenobarbital/primidone | ↔ | ↓
Phenytoin (PHT) | ↔ | ↓
Pregabalin | ↔ | ↔
Rifampin | Not assessed | ↓
Topiramate | ↔ [Slight increase not expected to be clinically relevant.] | ↔
Valproate | ↓ | ↑
Valproate + PHT and/or CBZ | Not assessed | ↔
Zonisamide | Not assessed | ↔
↔ = No significant effect.
? = Conflicting data.

Estrogen-Containing Oral Contraceptives: In 16 female volunteers, an oral contraceptive preparation containing 30 mcg ethinylestradiol and 150 mcg levonorgestrel increased the apparent clearance of lamotrigine (300 mg/day) by approximately 2-fold with a mean decrease in AUC of 52% and in Cmax of 39%. In this study, trough serum lamotrigine concentrations gradually increased and were approximately 2-fold higher on average at the end of the week of the inactive hormone preparation compared with trough lamotrigine concentrations at the end of the active hormone cycle.

Gradual transient increases in lamotrigine plasma levels (approximate 2-fold increase) occurred during the week of inactive hormone preparation ("pill-free" week) for women not also taking a drug that increased the clearance of lamotrigine (carbamazepine, phenytoin, phenobarbital, primidone, or rifampin). The increase in lamotrigine plasma levels will be greater if the dose of LAMOTRIGINE is increased in the few days before or during the "pill-free" week. Increases in lamotrigine plasma levels could result in dose-dependent adverse effects. In the same study, coadministration of LAMOTRIGINE (300 mg/day) in 16 female volunteers did not affect the pharmacokinetics of the ethinylestradiol component of the oral contraceptive preparation. There were mean decreases in the AUC and Cmax of the levonorgestrel component of 19% and 12%, respectively. Measurement of serum progesterone indicated that there was no hormonal evidence of ovulation in any of the 16 volunteers, although measurement of serum FSH, LH, and estradiol indicated that there was some loss of suppression of the hypothalamic-pituitary-ovarian axis.

The effects of doses of LAMOTRIGINE other than 300 mg/day have not been systematically evaluated in controlled clinical trials.

The clinical significance of the observed hormonal changes on ovulatory activity is unknown. However, the possibility of decreased contraceptive efficacy in some patients cannot be excluded. Therefore, patients should be instructed to promptly report changes in their menstrual pattern (e.g., break-through bleeding).

Dosage adjustments may be necessary for women receiving estrogen-containing oral contraceptive preparations [see Dosage and Administration (2.1)].

Other Hormonal Contraceptives or Hormone Replacement Therapy: The effect of other hormonal contraceptive preparations or hormone replacement therapy on the pharmacokinetics of lamotrigine has not been systematically evaluated. It has been reported that ethinylestradiol, not progestogens, increased the clearance of lamotrigine up to 2-fold, and the progestin-only pills had no effect on lamotrigine plasma levels. Therefore, adjustments to the dosage of LAMOTRIGINE in the presence of progestogens alone will likely not be needed.

Bupropion: The pharmacokinetics of a 100-mg single dose of LAMOTRIGINE in healthy volunteers (n = 12) were not changed by coadministration of bupropion sustained-release formulation (150 mg twice a day) starting 11 days before LAMOTRIGINE.

Carbamazepine: LAMOTRIGINE has no appreciable effect on steady-state carbamazepine plasma concentration. Limited clinical data suggest there is a higher incidence of dizziness, diplopia, ataxia, and blurred vision in patients receiving carbamazepine with lamotrigine than in patients receiving other AEDs with lamotrigine [see Adverse Reactions (6.1)]. The mechanism of this interaction is unclear. The effect of lamotrigine on plasma concentrations of carbamazepine-epoxide is unclear. In a small subset of patients (n = 7) studied in a placebo-controlled trial, lamotrigine had no effect on carbamazepine-epoxide plasma concentrations, but in a small, uncontrolled study (n = 9), carbamazepine-epoxide levels increased.

The addition of carbamazepine decreases lamotrigine steady-state concentrations by approximately 40%.

Felbamate: In a study of 21 healthy volunteers, coadministration of felbamate (1,200 mg twice daily) with lamotrigine (100 mg twice daily for 10 days) appeared to have no clinically relevant effects on the pharmacokinetics of lamotrigine.

Folate Inhibitors: Lamotrigine is a weak inhibitor of dihydrofolate reductase. Prescribers should be aware of this action when prescribing other medications that inhibit folate metabolism.

Gabapentin: Based on a retrospective analysis of plasma levels in 34 patients who received lamotrigine both with and without gabapentin, gabapentin does not appear to change the apparent clearance of lamotrigine.

Levetiracetam: Potential drug interactions between levetiracetam and lamotrigine were assessed by evaluating serum concentrations of both agents during placebo-controlled clinical trials. These data indicate that lamotrigine does not influence the pharmacokinetics of levetiracetam and that levetiracetam does not influence the pharmacokinetics of lamotrigine.

Lithium: The pharmacokinetics of lithium were not altered in healthy subjects (n = 20) by coadministration of lamotrigine (100 mg/day) for 6 days.

Olanzapine: The AUC and Cmax of olanzapine were similar following the addition of olanzapine (15 mg once daily) to lamotrigine (200 mg once daily) in healthy male volunteers (n = 16) compared with the AUC and Cmax in healthy male volunteers receiving olanzapine alone (n = 16).

In the same study, the AUC and Cmax of lamotrigine were reduced on average by 24% and 20%, respectively, following the addition of olanzapine to lamotrigine in healthy male volunteers compared with those receiving lamotrigine alone. This reduction in lamotrigine plasma concentrations is not expected to be clinically relevant.

Oxcarbazepine: The AUC and Cmax of oxcarbazepine and its active 10-monohydroxy oxcarbazepine metabolite were not significantly different following the addition of oxcarbazepine (600 mg twice daily) to lamotrigine (200 mg once daily) in healthy male volunteers (n = 13) compared with healthy male volunteers receiving oxcarbazepine alone (n = 13).

In the same study, the AUC and Cmax of lamotrigine were similar following the addition of oxcarbazepine (600 mg twice daily) to LAMOTRIGINE in healthy male volunteers compared with those receiving LAMOTRIGINE alone. Limited clinical data suggest a higher incidence of headache, dizziness, nausea, and somnolence with coadministration of lamotrigine and oxcarbazepine compared with lamotrigine alone or oxcarbazepine alone.

Phenobarbital, Primidone: The addition of phenobarbital or primidone decreases lamotrigine steady-state concentrations by approximately 40%.

Phenytoin: Lamotrigine has no appreciable effect on steady-state phenytoin plasma concentrations in patients with epilepsy. The addition of phenytoin decreases lamotrigine steady-state concentrations by approximately 40%.

Pregabalin: Steady-state trough plasma concentrations of lamotrigine were not affected by concomitant pregabalin (200 mg 3 times daily) administration. There are no pharmacokinetic interactions between lamotrigine and pregabalin.

Rifampin: In 10 male volunteers, rifampin (600 mg/day for 5 days) significantly increased the apparent clearance of a single 25-mg dose of lamotrigine by approximately 2-fold (AUC decreased by approximately 40%).

Topiramate: Topiramate resulted in no change in plasma concentrations of lamotrigine. Administration of lamotrigine resulted in a 15% increase in topiramate concentrations.

Valproate: When lamotrigine was administered to healthy volunteers (n = 18) receiving valproate, the trough steady-state valproate plasma concentrations decreased by an average of 25% over a 3-week period, and then stabilized. However, adding lamotrigine to the existing therapy did not cause a change in valproate plasma concentrations in either adult or pediatric patients in controlled clinical trials.

The addition of valproate increased lamotrigine steady-state concentrations in normal volunteers by slightly more than 2-fold. In one study, maximal inhibition of lamotrigine clearance was reached at valproate doses between 250 mg/day and 500 mg/day and did not increase as the valproate dose was further increased.

Zonisamide: In a study of 18 patients with epilepsy, coadministration of zonisamide (200 to 400 mg/day) with lamotrigine (150 to 500 mg/day for 35 days) had no significant effect on the pharmacokinetics of lamotrigine.

Known Inducers or Inhibitors of Glucuronidation: Drugs other than those listed above have not been systematically evaluated in combination with lamotrigine. Since lamotrigine is metabolized predominately by glucuronic acid conjugation, drugs that are known to induce or inhibit glucuronidation may affect the apparent clearance of lamotrigine and doses of lamotrigine may require adjustment based on clinical response.

Other: Results of in vitro experiments suggest that clearance of lamotrigine is unlikely to be reduced by concomitant administration of amitriptyline, clonazepam, clozapine, fluoxetine, haloperidol, lorazepam, phenelzine, risperidone, sertraline, or trazodone).

Results of in vitro experiments suggest that lamotrigine does not reduce the clearance of drugs eliminated predominantly by CYP2D6.

Special Populations: Patients With Renal Impairment: Twelve volunteers with chronic renal failure (mean creatinine clearance: 13 mL/min; range: 6 to 23) and another 6 individuals undergoing hemodialysis were each given a single 100-mg dose of lamotrigine. The mean plasma half-lives determined in the study were 42.9 hours (chronic renal failure), 13.0 hours (during hemodialysis), and 57.4 hours (between hemodialysis) compared with 26.2 hours in healthy volunteers. On average, approximately 20% (range: 5.6 to 35.1) of the amount of lamotrigine present in the body was eliminated by hemodialysis during a 4-hour session [see Dosage and Administration (2.1)].

Hepatic Disease: The pharmacokinetics of lamotrigine following a single 100-mg dose of lamotrigine were evaluated in 24 subjects with mild, moderate, and severe hepatic impairment (Child-Pugh Classification system) and compared with 12 subjects without hepatic impairment. The patients with severe hepatic impairment were without ascites (n = 2) or with ascites (n = 5). The mean apparent clearances of lamotrigine in patients with mild (n = 12), moderate (n = 5), severe without ascites (n = 2), and severe with ascites (n = 5) liver impairment were 0.30 ± 0.09, 0.24 ± 0.1, 0.21 ± 0.04, and 0.15 ± 0.09 mL/min/kg, respectively, as compared with 0.37 ± 0.1 mL/min/kg in the healthy controls. Mean half-life of lamotrigine in patients with mild, moderate, severe without ascites, and severe with ascites hepatic impairment were 46 ± 20, 72 ± 44, 67 ± 11, and 100 ± 48 hours, respectively, as compared with 33 ± 7 hours in healthy controls [see Dosage and Administration (2.1)].

Age: Pediatric Patients: The pharmacokinetics of lamotrigine following a single 2-mg/kg dose were evaluated in 2 studies of pediatric patients (n = 29 for patients 10 months to 5.9 years of age and n = 26 for patients 5 to 11 years of age). Forty-three patients received concomitant therapy with other AEDs and 12 patients received lamotrigine as monotherapy. Lamotrigine pharmacokinetic parameters for pediatric patients are summarized in Table 16.

Population pharmacokinetic analyses involving patients 2 to 18 years of age demonstrated that lamotrigine clearance was influenced predominantly by total body weight and concurrent AED therapy. The oral clearance of lamotrigine was higher, on a body weight basis, in pediatric patients than in adults. Weight-normalized lamotrigine clearance was higher in those subjects weighing less than 30 kg, compared with those weighing greater than 30 kg. Accordingly, patients weighing less than 30 kg may need an increase of as much as 50% in maintenance doses, based on clinical response, as compared with subjects weighing more than 30 kg being administered the same AEDs [see Dosage and Administration (2.2)]. These analyses also revealed that, after accounting for body weight, lamotrigine clearance was not significantly influenced by age. Thus, the same weight-adjusted doses should be administered to children irrespective of differences in age. Concomitant AEDs which influence lamotrigine clearance in adults were found to have similar effects in children.

Table 16. Mean Pharmacokinetic Parameters in Pediatric Patients With Epilepsy
Pediatric Study Population | Number of Subjects | Tmax (hr) | t½ (hr) | Cl/F (mL/min/kg)
Ages 10 months-5.3 years
Patients taking carbamazepine, phenytoin, phenobarbital, or primidone [Carbamazepine, phenobarbital, phenytoin, and primidone have been shown to increase the apparent clearance of lamotrigine. Estrogen-containing oral contraceptives and rifampin have also been shown to increase the apparent clearance of lamotrigine [see Drug Interactions (7)].] | 10 | 3.0 (1.0-5.9) | 7.7 (5.7-11.4) | 3.62 (2.44-5.28)
Patients taking AEDs with no known effect on the apparent clearance of lamotrigine | 7 | 5.2 (2.9-6.1) | 19.0 (12.9-27.1) | 1.2 (0.75-2.42)
Patients taking valproate only | 8 | 2.9 (1.0-6.0) | 44.9 (29.5-52.5) | 0.47 (0.23-0.77)
Ages 5-11 years
Patients taking carbamazepine, phenytoin, phenobarbital, or primidone | 7 | 1.6 (1.0-3.0) | 7.0 (3.8-9.8) | 2.54 (1.35-5.58)
Patients taking carbamazepine, phenytoin, phenobarbital, or primidone plus valproate | 8 | 3.3 (1.0-6.4) | 19.1 (7.0-31.2) | 0.89 (0.39-1.93)
Patients taking valproate only [Two subjects were included in the calculation for mean Tmax.] | 3 | 4.5 (3.0-6.0) | 65.8 (50.7-73.7) | 0.24 (0.21-0.26)
Ages 13-18 years
Patients taking carbamazepine, phenytoin, phenobarbital, or primidone | 11 | [Parameter not estimated.] |  | 1.3
Patients taking carbamazepine, phenytoin, phenobarbital, or primidone* plus valproate | 8 |  |  | 0.5
Patients taking valproate only | 4 |  |  | 0.3

Elderly: The pharmacokinetics of lamotrigine following a single 150-mg dose of LAMOTRIGINE were evaluated in 12 elderly volunteers between the ages of 65 and 76 years (mean creatinine clearance = 61 mL/min, range: 33 to 108 mL/min). The mean half-life of lamotrigine in these subjects was 31.2 hours (range: 24.5 to 43.4 hours), and the mean clearance was 0.40 mL/min/kg (range: 0.26 to 0.48 mL/min/kg).

Gender: The clearance of lamotrigine is not affected by gender. However, during dose escalation of LAMOTRIGINE in one clinical trial in patients with epilepsy on a stable dose of valproate (n = 77), mean trough lamotrigine concentrations, unadjusted for weight, were 24% to 45% higher (0.3 to 1.7 mcg/mL) in females than in males.

Race: The apparent oral clearance of lamotrigine was 25% lower in non-Caucasians than Caucasians.

13 NONCLINICAL TOXICOLOGY

13.1 Carcinogenesis, Mutagenesis, Impairment of Fertility

No evidence of carcinogenicity was seen in 1 mouse study or 2 rat studies following oral administration of lamotrigine for up to 2 years at maximum tolerated doses (30 mg/kg/day for mice and 10 to 15 mg/kg/day for rats, doses that are equivalent to 90 mg/m^2 and 60 to 90 mg/m^2, respectively). Steady-state plasma concentrations ranged from 1 to 4 mcg/mL in the mouse study and 1 to 10 mcg/mL in the rat study. Plasma concentrations associated with the recommended human doses of 300 to 500 mg/day are generally in the range of 2 to 5 mcg/mL, but concentrations as high as 19 mcg/mL have been recorded.

Lamotrigine was not mutagenic in the presence or absence of metabolic activation when tested in 2 gene mutation assays (the Ames test and the in vitro mammalian mouse lymphoma assay). In 2 cytogenetic assays (the in vitro human lymphocyte assay and the in vivo rat bone marrow assay), lamotrigine did not increase the incidence of structural or numerical chromosomal abnormalities.

No evidence of impairment of fertility was detected in rats given oral doses of lamotrigine up to 2.4 times the highest usual human maintenance dose of 8.33 mg/kg/day or 0.4 times the human dose on a mg/m^2 basis. The effect of lamotrigine on human fertility is unknown.

14 CLINICAL STUDIES

14.1 Epilepsy

Monotherapy With LAMOTRIGINE in Adults With Partial Seizures Already Receiving Treatment With Carbamazepine, Phenytoin, Phenobarbital, or Primidone as the Single AED: The effectiveness of monotherapy with LAMOTRIGINE was established in a multicenter, double-blind clinical trial enrolling 156 adult outpatients with partial seizures. The patients experienced at least 4 simple partial, complex partial, and/or secondarily generalized seizures during each of 2 consecutive 4-week periods while receiving carbamazepine or phenytoin monotherapy during baseline. LAMOTRIGINE (target dose of 500 mg/day) or valproate (1,000 mg/day) was added to either carbamazepine or phenytoin monotherapy over a 4-week period. Patients were then converted to monotherapy with LAMOTRIGINE or valproate during the next 4 weeks, then continued on monotherapy for an additional 12-week period.

Study endpoints were completion of all weeks of study treatment or meeting an escape criterion. Criteria for escape relative to baseline were: (1) doubling of average monthly seizure count, (2) doubling of highest consecutive 2-day seizure frequency, or (3) emergence of a new seizure type (defined as a seizure that did not occur during the 8-week baseline) that is more severe than seizure types that occur during study treatment. The primary efficacy variable was the proportion of patients in each treatment group who met escape criteria.

The percentages of patients who met escape criteria were 42% (32/76) in the group receiving LAMOTRIGINE and 69% (55/80) in the valproate group. The difference in the percentage of patients meeting escape criteria was statistically significant (p= 0.0012) in favor of LAMOTRIGINE. No differences in efficacy based on age, sex, or race were detected.

Patients in the control group were intentionally treated with a relatively low dose of valproate; as such, the sole objective of this study was to demonstrate the effectiveness and safety of monotherapy with LAMOTRIGINE, and cannot be interpreted to imply the superiority of LAMOTRIGINE to an adequate dose of valproate.

Adjunctive Therapy With LAMOTRIGINE in Adults With Partial Seizures: The effectiveness of LAMOTRIGINE as adjunctive therapy (added to other AEDs) was established in 3 multicenter, placebo-controlled, double-blind clinical trials in 355 adults with refractory partial seizures. The patients had a history of at least 4 partial seizures per month in spite of receiving one or more AEDs at therapeutic concentrations and, in 2 of the studies, were observed on their established AED regimen during baselines that varied between 8 to 12 weeks. In the third, patients were not observed in a prospective baseline. In patients continuing to have at least 4 seizures per month during the baseline, LAMOTRIGINE or placebo was then added to the existing therapy. In all 3 studies, change from baseline in seizure frequency was the primary measure of effectiveness. The results given below are for all partial seizures in the intent-to-treat population (all patients who received at least one dose of treatment) in each study, unless otherwise indicated. The median seizure frequency at baseline was 3 per week while the mean at baseline was 6.6 per week for all patients enrolled in efficacy studies.

One study (n = 216) was a double-blind, placebo-controlled, parallel trial consisting of a 24-week treatment period. Patients could not be on more than 2 other anticonvulsants and valproate was not allowed. Patients were randomized to receive placebo, a target dose of 300 mg/day of LAMOTRIGINE, or a target dose of 500 mg/day of LAMOTRIGINE. The median reductions in the frequency of all partial seizures relative to baseline were 8% in patients receiving placebo, 20% in patients receiving 300 mg/day of LAMOTRIGINE, and 36% in patients receiving 500 mg/day of LAMOTRIGINE. The seizure frequency reduction was statistically significant in the 500-mg/day group compared with the placebo group, but not in the 300-mg/day group.

A second study (n = 98) was a double-blind, placebo-controlled, randomized, crossover trial consisting of two 14-week treatment periods (the last 2 weeks of which consisted of dose tapering) separated by a 4-week washout period. Patients could not be on more than 2 other anticonvulsants and valproate was not allowed. The target dose of LAMOTRIGINE was 400 mg/day. When the first 12 weeks of the treatment periods were analyzed, the median change in seizure frequency was a 25% reduction on LAMOTRIGINE compared with placebo (p<0.001).

The third study (n = 41) was a double-blind, placebo-controlled, crossover trial consisting of two 12-week treatment periods separated by a 4-week washout period. Patients could not be on more than 2 other anticonvulsants. Thirteen patients were on concomitant valproate; these patients received 150 mg/day of LAMOTRIGINE. The 28 other patients had a target dose of 300 mg/day of LAMOTRIGINE. The median change in seizure frequency was a 26% reduction on LAMOTRIGINE compared with placebo (p<0.01).

No differences in efficacy based on age, sex, or race, as measured by change in seizure frequency, were detected.

Adjunctive Therapy With LAMOTRIGINE in Pediatric Patients With Partial Seizures: The effectiveness of LAMOTRIGINE as adjunctive therapy in pediatric patients with partial seizures was established in a multicenter, double-blind, placebo-controlled trial in 199 patients 2 to 16 years of age (n = 98 on LAMOTRIGINE, n = 101 on placebo). Following an 8-week baseline phase, patients were randomized to 18 weeks of treatment with LAMOTRIGINE or placebo added to their current AED regimen of up to 2 drugs. Patients were dosed based on body weight and valproate use. Target doses were designed to approximate 5 mg/kg/day for patients taking valproate (maximum dose: 250 mg/day) and 15 mg/kg/day for the patients not taking valproate (maximum dose: 750 mg/day). The primary efficacy endpoint was percentage change from baseline in all partial seizures. For the intent-to-treat population, the median reduction of all partial seizures was 36% in patients treated with LAMOTRIGINE and 7% on placebo, a difference that was statistically significant (p<0.01).

Adjunctive Therapy With LAMOTRIGINE in Pediatric and Adult Patients With Lennox-Gastaut Syndrome: The effectiveness of LAMOTRIGINE as adjunctive therapy in patients with Lennox-Gastaut syndrome was established in a multicenter, double-blind, placebo-controlled trial in 169 patients 3 to 25 years of age (n = 79 on LAMOTRIGINE, n = 90 on placebo). Following a 4-week single-blind, placebo phase, patients were randomized to 16 weeks of treatment with LAMOTRIGINE or placebo added to their current AED regimen of up to 3 drugs. Patients were dosed on a fixed-dose regimen based on body weight and valproate use. Target doses were designed to approximate 5 mg/kg/day for patients taking valproate (maximum dose: 200 mg/day) and 15 mg/kg/day for patients not taking valproate (maximum dose: 400 mg/day). The primary efficacy endpoint was percentage change from baseline in major motor seizures (atonic, tonic, and major myoclonic). For the intent-to-treat population, the median reduction of major motor seizures was 32% in patients treated with LAMOTRIGINE and 9% on placebo, a difference that was statistically significant (p<0.05). Drop attacks were significantly reduced by LAMOTRIGINE (34%) compared with placebo (9%).

14.2 Bipolar Disorder

The effectiveness of LAMOTRIGINE in the maintenance treatment of Bipolar I Disorder was established in 2 multicenter, double-blind, placebo-controlled studies in adult patients who met DSM-IV criteria for Bipolar I Disorder. Study 1 enrolled patients with a current or recent (within 60 days) depressive episode as defined by DSM-IV and Study 2 included patients with a current or recent (within 60 days) episode of mania or hypomania as defined by DSM-IV. Both studies included a cohort of patients (30% of 404 patients in Study 1 and 28% of 171 patients in Study 2) with rapid cycling Bipolar Disorder (4 to 6 episodes per year).

In both studies, patients were titrated to a target dose of 200 mg of LAMOTRIGINE, as add-on therapy or as monotherapy, with gradual withdrawal of any psychotropic medications during an 8- to 16-week open-label period. Overall 81% of 1,305 patients participating in the open-label period were receiving 1 or more other psychotropic medications, including benzodiazepines, selective serotonin reuptake inhibitors (SSRIs), atypical antipsychotics (including olanzapine), valproate, or lithium, during titration of LAMOTRIGINE. Patients with a CGI-severity score of 3 or less maintained for at least 4 continuous weeks, including at least the final week on monotherapy with LAMOTRIGINE, were randomized to a placebo-controlled, double-blind treatment period for up to 18 months. The primary endpoint was TIME (time to intervention for a mood episode or one that was emerging, time to discontinuation for either an adverse event that was judged to be related to Bipolar Disorder, or for lack of efficacy). The mood episode could be depression, mania, hypomania, or a mixed episode.

In Study 1, patients received double-blind monotherapy with LAMOTRIGINE 50 mg/day (n = 50), LAMOTRIGINE 200 mg/day (n = 124), LAMOTRIGINE 400 mg/day (n = 47), or placebo (n = 121). LAMOTRIGINE (200- and 400-mg/day treatment groups combined) was superior to placebo in delaying the time to occurrence of a mood episode. Separate analyses of the 200- and 400-mg/day dose groups revealed no added benefit from the higher dose.

In Study 2, patients received double-blind monotherapy with LAMOTRIGINE (100 to 400 mg/day, n = 59), or placebo (n = 70). LAMOTRIGINE was superior to placebo in delaying time to occurrence of a mood episode. The mean dose of LAMOTRIGINE was about 211 mg/day.

Although these studies were not designed to separately evaluate time to the occurrence of depression or mania, a combined analysis for the 2 studies revealed a statistically significant benefit for LAMOTRIGINE over placebo in delaying the time to occurrence of both depression and mania, although the finding was more robust for depression.

16 HOW SUPPLIED/STORAGE AND HANDLING

Lamotrigine Tablets 25 mg:

Round, white tablets, scored on one side, embossed with "TARO" on one side and on the other side "LMT" above score and "25" below the score.

Bottles of 60. . . . . . . . . . . . . . . . . . . . . . . . . NDC 21695-227-60

Store at 20°-25°C (68°-77°F)[see USP Controlled Room Temperature] in a dry place.

Lamotrigine Tablets 100 mg:

Round, light peach, scored tablets, embossed with "TARO" on one side and on the other side "LMT" above score and 100 below the score.

Bottles of 30. . . . . . . . . . . . . . . . . . . . . . . . . NDC 21695-228-30
Bottles of 60. . . . . . . . . . . . . . . . . . . . . . ... . NDC 21695-228-60

Lamotrigine Tablets 150 mg:

Round, cream tablets, scored on one side, embossed with "TARO" on one side and on the other side "LMT" above score and 150 below the score.

Bottles of 60. . . . . . . . . . . . . . . . . . . . . . . . . NDC 21695-107-60

Lamotrigine Tablets 200 mg:

Round, light blue tablets, scored on one side, embossed with "TARO" on one side and on the other side "LMT" above score and 200 below the score.

Bottles of 60. . . . . . . . . . . . . . . . . . . . . . . . . NDC 21695-229-60

Store at 20°-25°C (68°-77°F) [see USP Controlled Room Temperature] in a dry place and protect from light.

17 PATIENT COUNSELING INFORMATION

See Medication Guide that accompanies the product.

17.1 Rash

Prior to initiation of treatment with LAMOTRIGINE, the patient should be instructed that a rash or other signs or symptoms of hypersensitivity (e.g., fever, lymphadenopathy) may herald a serious medical event and that the patient should report any such occurrence to a physician immediately.

17.2 Suicidal Thinking and Behavior

Patients, their caregivers, and families should be counseled that AEDs, including LAMOTRIGINE, may increase the risk of suicidal thoughts and behavior and should be advised of the need to be alert for the emergence or worsening of symptoms of depression, any unusual changes in mood or behavior, or the emergence of suicidal thoughts, behavior, or thoughts about self-harm. Behaviors of concern should be reported immediately to healthcare providers.

17.3 Worsening of Seizures

Patients should be advised to notify their physician if worsening of seizure control occurs.

17.4 CNS Adverse Effects

Patients should be advised that LAMOTRIGINE may cause dizziness, somnolence, and other symptoms and signs of central nervous system (CNS) depression. Accordingly, they should be advised neither to drive a car nor to operate other complex machinery until they have gained sufficient experience on LAMOTRIGINE to gauge whether or not it adversely affects their mental and/or motor performance.

17.5 Blood Dyscrasias and/or Acute Multiorgan Failure

Patients should be advised of the possibility of blood dyscrasias and/or acute multiorgan failure and to contact their physician immediately if they experience any signs or symptoms of these conditions [see Warnings and Precautions (5.3, 5.4)].

17.6 Pregnancy

Patients should be advised to notify their physicians if they become pregnant or intend to become pregnant during therapy. Patients should be advised to notify their physicians if they intend to breastfeed or are breastfeeding an infant.

Patients should also be encouraged to enroll in the North American Antiepileptic Drug (NAAED) Pregnancy Registry if they become pregnant. This registry is collecting information about the safety of antiepileptic drugs during pregnancy. To enroll, patients can call the toll-free number 1-888-233-2334 [see Use in Specific Populations (8.1)].

17.7 Oral Contraceptive Use

Women should be advised to notify their physician if they plan to start or stop use of oral contraceptives or other female hormonal preparations. Starting estrogen-containing oral contraceptives may significantly decrease lamotrigine plasma levels and stopping estrogen-containing oral contraceptives (including the "pill-free" week) may significantly increase lamotrigine plasma levels [see Warnings and Precautions (5.8), Clinical Pharmacology (12.3)]. Women should also be advised to promptly notify their physician if they experience adverse events or changes in menstrual pattern (e.g., break-through bleeding) while receiving LAMOTRIGINE in combination with these medications.

17.8 Discontinuing LAMOTRIGINE

Patients should be advised to notify their physician if they stop taking LAMOTRIGINE for any reason and not to resume LAMOTRIGINE without consulting their physician.

17.9 Potential Medication Errors

Medication errors involving LAMOTRIGINE have occurred. In particular the name LAMOTRIGINE can be confused with the names of other commonly used medications. Medication errors may also occur between the different formulations of LAMOTRIGINE. To reduce the potential of medication errors, write and say LAMOTRIGINE clearly. Depictions of the LAMOTRIGINE Tablets can be found in the Medication Guide that accompanies the product to highlight the distinctive markings, colors, and shapes that serve to identify the different presentations of the drug and thus may help reduce the risk of medication errors. To avoid a medication error of using the wrong drug or formulation, patients should be strongly advised to visually inspect their tablets to verify that they are LAMOTRIGINE, as well as the correct formulation of LAMOTRIGINE, each time they fill their prescription [see Dosage Forms and Strengths (3.1,3.2, 3.3), How Supplied/Storage and Handling (16)].

Mfd. by: Taro Pharmaceutical Industries Ltd., Haifa Bay, Israel 26110
Dist. by: Taro Pharmaceuticals U.S.A., Inc., Hawthorne, NY 10532
Repackaged by: Rebel Distributors Corp, Thousand Oaks, CA 91320

Revised: September, 2009
70496-0909-2

MEDICATION GUIDE
LAMOTRIGINE (lamotrigine) Tablets

Read this Medication Guide before you start taking LAMOTRIGINE and each time you get a refill. There may be new information. This information does not take the place of talking with your healthcare provider about your medical condition or treatment. If you have questions about LAMOTRIGINE, ask your healthcare provider or pharmacist. What is the most important information I should know about LAMOTRIGINE?

1. LAMOTRIGINE may cause a serious skin rash that may cause you to be hospitalized or to stop LAMOTRIGINE; it may rarely cause death.

There is no way to tell if a mild rash will develop into a more serious reaction. These serious skin reactions are more likely to happen when you begin taking LAMOTRIGINE, within the first 2 to 8 weeks of treatment. But it can happen in people who have taken LAMOTRIGINE for any period of time. Children between 2 to 16 years of age have a higher chance of getting this serious skin reaction while taking LAMOTRIGINE.

The risk of getting a rash is higher if you:

- take LAMOTRIGINE while taking valproate (DEPAKENE (valproic acid) or DEPAKOTE (divalproex sodium))
- take a higher starting dose of LAMOTRIGINE than your healthcare provider prescribed
- increase your dose of LAMOTRIGINE faster than prescribed.

LAMOTRIGINE can also cause other types of allergic reactions or serious problems which may affect organs and other parts of your body like the liver or blood cells. You may or may not have a rash with these types of reactions. Call your healthcare provider right away if you have any of the following:
  - a skin rash
  - hives
  - fever
  - swollen lymph glands
  - painful sores in the mouth or around your eyes
  - swelling of your lips or tongue
  - yellowing of your skin or eyes
  - unusual bruising or bleeding
  - severe fatigue or weakness
  - severe muscle pain
  - frequent infections
These symptoms may be the first signs of a serious reaction. A healthcare provider should examine you to decide if you should continue taking LAMOTRIGINE.

2. Like other antiepileptic drugs, LAMOTRIGINE may cause suicidal thoughts or actions in a very small number of people, about 1 in 500.

Call a healthcare provider right away if you have any of these symptoms, especially if they are new, worse, or worry you:

- thoughts about suicide or dying
- attempt to commit suicide
- new or worse depression
- new or worse anxiety
- feeling agitated or restless
- panic attacks
- trouble sleeping (insomnia)
- new or worse irritability
- acting aggressive, being angry, or violent
- acting on dangerous impulses
- an extreme increase in activity and talking (mania)
- other unusual changes in behavior or mood
  Do not stop LAMOTRIGINE without first talking to a healthcare provider.
- Stopping LAMOTRIGINE suddenly can cause serious problems.
- Suicidal thoughts or actions can be caused by things other than medicines. If you have suicidal thoughts or actions, your healthcare provider may check for other causes.
  How can I watch for early symptoms of suicidal thoughts and actions?
- Pay attention to any changes, especially sudden changes, in mood, behaviors, thoughts, or feelings.
- Keep all follow-up visits with your healthcare provider as scheduled.
- Call your healthcare provider between visits as needed, especially if you are worried about symptoms.
  LAMOTRIGINE can have other serious side effects. For more information ask your healthcare provider or pharmacist. Tell your healthcare provider if you have any side effect that bothers you. Be sure to read the section below entitled "What are the possible side effects of LAMOTRIGINE?"

3. Patients prescribed LAMOTRIGINE have sometimes been given the wrong medicine because many medicines have names similar to LAMOTRIGINE, so always check that you receive LAMOTRIGINE.

Taking the wrong medication can cause serious health problems. When your healthcare provider gives you a prescription for LAMOTRIGINE:

- Make sure you can read it clearly.
- Talk to your pharmacist to check that you are given the correct medicine.
- Each time you fill your prescription, check the tablets you receive against the pictures of the tablets below.

These pictures show the distinct wording, colors, and shapes of the tablets that help to identify the right strength of LAMOTRIGINE Tablets, Chewable Dispersible Tablets, and Orally Disintegrating Tablets. Immediately call your pharmacist if you receive a LAMOTRIGINE tablet that does not look like one of the tablets shown below, as you may have received the wrong medication.

LAMOTRIGINE Tablets

Lamotrigine Tablets 25 mg:
Round, white tablets, scored on one side, embossed with "TARO" on one side and on the other side "LMT" above score and "25" below the score.

Lamotrigine Tablets 100 mg:
Round, light peach, scored tablets, embossed with "TARO" on one side and on the other side "LMT" above score and 100 below the score.

Lamotrigine Tablets 150 mg:
Round, cream tablets, scored on one side, embossed with "TARO" on one side and on the other side "LMT" above score and 150 below the score.

Lamotrigine Tablets 200 mg:
Round, light blue tablets, scored on one side, embossed with "TARO" on one side and on the other side "LMT" above score and 200 below the score.

What is LAMOTRIGINE?

LAMOTRIGINE is a prescription medicine used:

1. together with other medicines to treat certain types of seizures (partial seizures, primary generalized tonic-clonic seizures, generalized seizures of Lennox-Gastaut syndrome) in people 2 years or older.
2. alone when changing from other medicines used to treat partial seizures in people 16 years or older.
3. for the long-term treatment of Bipolar I Disorder to lengthen the time between mood episodes in people 18 years or older who have been treated for mood episodes with other medicine.

It is not known if LAMOTRIGINE is safe or effective in children or teenagers under the age of 18 with mood disorders such as bipolar disorder or depression.

It is not known if LAMOTRIGINE is safe or effective when used alone as the first treatment of seizures in adults.

Who should not take LAMOTRIGINE?

You should not take LAMOTRIGINE if you have had an allergic reaction to lamotrigine or to any of the inactive ingredients in LAMOTRIGINE. See the end of this leaflet for a complete list of ingredients in LAMOTRIGINE.

What should I tell my healthcare provider before taking LAMOTRIGINE?

Before taking LAMOTRIGINE, tell your healthcare provider about all of your medical conditions, including if you:

- have had a rash or allergic reaction to another antiseizure medicine.
- have or have had depression, mood problems or suicidal thoughts or behavior.
- are taking oral contraceptives (birth control pills) or other female hormonal medicines. Do not start or stop taking birth control pills or other female hormonal medicine until you have talked with your healthcare provider. Tell your healthcare provider if you have any changes in your menstrual pattern such as breakthrough bleeding. Stopping or starting these medicines may cause side effects (such as dizziness, lack of coordination, or double vision) or lessen how well LAMOTRIGINE works.
- are pregnant or plan to become pregnant. It is not known if LAMOTRIGINE will harm your unborn baby. If you become pregnant while taking LAMOTRIGINE, talk to your healthcare provider about registering with the North American Antiepileptic Drug Pregnancy Registry. You can enroll in this registry by calling 1-888-233-2334. The purpose of this registry is to collect information about the safety of antiepileptic drugs during pregnancy.
- are breastfeeding. LAMOTRIGINE can pass into your breast milk. You and your healthcare provider should decide if you should take LAMOTRIGINE or breastfeed. Breastfeeding while taking LAMOTRIGINE is not recommended.

Tell your healthcare provider about all the medicines you take or if you are planning to take a new medicine, including prescription and non-prescription medicines, vitamins, and herbal supplements. Using LAMOTRIGINE with certain other medicines can affect each other, causing side effects.

How should I take LAMOTRIGINE?

- Take LAMOTRIGINE exactly as prescribed.
- Your healthcare provider may change your dose. Do not change your dose without talking to your healthcare provider.
- Do not stop taking LAMOTRIGINE without talking to your healthcare provider. Stopping LAMOTRIGINE suddenly may cause serious problems. For example, if you have epilepsy and you stop taking LAMOTRIGINE suddenly, you may get seizures that do not stop. Talk with your healthcare provider about how to stop LAMOTRIGINE slowly.
- If you miss a dose of LAMOTRIGINE, take it as soon as you remember. If it is almost time for your next dose, just skip the missed dose. Take the next dose at your regular time. Do not take two doses at the same time.
- You may not feel the full effect of LAMOTRIGINE for several weeks.
- If you have epilepsy, tell your healthcare provider if your seizures get worse or if you have any new types of seizures.
- Swallow LAMOTRIGINE tablets whole.
- If you have trouble swallowing LAMOTRIGINE Tablets, there may be another form of LAMOTRIGINE you can take.
- If you receive LAMOTRIGINE in a blisterpack, examine the blisterpack before use. Do not use if blisters are torn, broken, or missing.

What should I avoid while taking LAMOTRIGINE?

- Do not drive a car or operate complex, hazardous machinery until you know how LAMOTRIGINE affects you.

What are possible side effects of LAMOTRIGINE?

- See "What is the most important information I should know about LAMOTRIGINE?" Common side effects of LAMOTRIGINE include:

• dizziness

• tremor

• headache

• rash

• blurred or double vision

• fever

• lack of coordination

• abdominal pain

• sleepiness

• back pain

• nausea, vomiting

• tiredness

• insomnia

• back pain

Tell your healthcare provider about any side effect that bothers you or that does not go away.

These are not all the possible side effects of LAMOTRIGINE. For more information, ask your healthcare provider or pharmacist.

Call your doctor for medical advice about side effects. You may report side effects to FDA at 1-800-FDA-1088.

How should I store LAMOTRIGINE?

- Store at 20°-25°C (68°-77°F)[see USP Controlled Room Temperature] in a dry place.
- Keep LAMOTRIGINE and all medicines out of the reach of children.

General information about LAMOTRIGINE

Medicines are sometimes prescribed for purposes other than those listed in a Medication Guide. Do not use LAMOTRIGINE for a condition for which it was not prescribed. Do not give LAMOTRIGINE to other people, even if they have the same symptoms you have. It may harm them.

This Medication Guide summarizes the most important information about LAMOTRIGINE. If you would like more information, talk with your healthcare provider. You can ask your healthcare provider or pharmacist for information about LAMOTRIGINE that is written for healthcare professionals.

What are the ingredients in LAMOTRIGINE?

LAMOTRIGINE Tablets

Active ingredient: lamotrigine.

Inactive ingredients: croscarmellose sodium, crospovidone, FD&C Blue #2 Aluminum Lake (200 mg strength only), FD&C Yellow No. 6 Lake (100 mg strength only), lactose monohydrate, magnesium stearate, microcrystalline cellulose, povidone, and yellow iron oxide (150 mg strength only).

This Medication Guide has been approved by the U.S. Food and Drug Administration.

DEPAKENE and DEPAKOTE are registered trademarks of Abbott Laboratories.

Mfd. by: Taro Pharmaceutical Industries Ltd., Haifa Bay, Israel 26110
Dist. by: Taro Pharmaceuticals U.S.A., Inc., Hawthorne, NY 10532
Revised: September, 2009
70496-0909-2